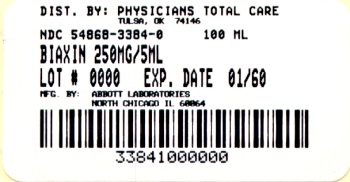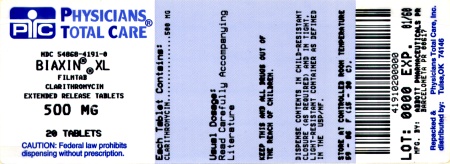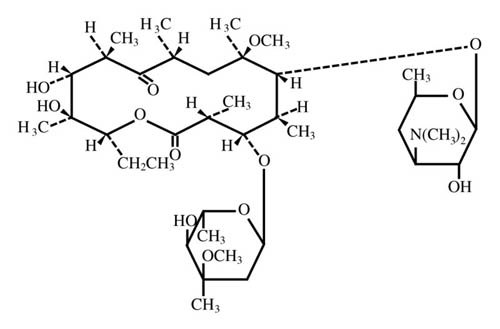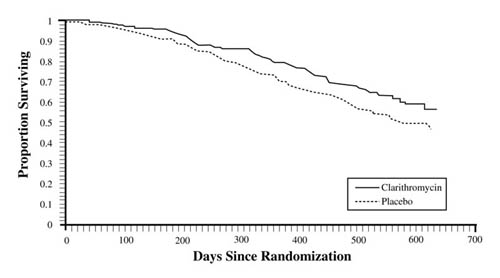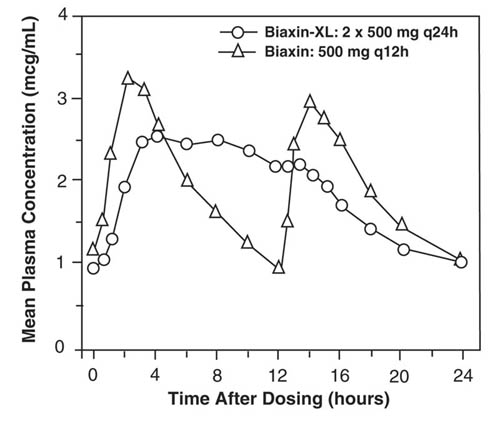 DRUG LABEL: Biaxin
NDC: 54868-3820 | Form: TABLET, FILM COATED
Manufacturer: Physicians Total Care, Inc.
Category: prescription | Type: HUMAN PRESCRIPTION DRUG LABEL
Date: 20120222

ACTIVE INGREDIENTS: CLARITHROMYCIN 250 mg/1 1
INACTIVE INGREDIENTS: HYDROXYPROPYL CELLULOSE; CROSCARMELLOSE SODIUM; D&C YELLOW NO. 10; FD&C BLUE NO. 1; MAGNESIUM STEARATE; POVIDONE; PROPYLENE GLYCOL; SILICON DIOXIDE; SORBIC ACID; SORBITAN MONOOLEATE; STEARIC ACID; TALC; TITANIUM DIOXIDE; VANILLIN; HYPROMELLOSES

BIAXIN® Filmtab®
(clarithromycin tablets, USP)
BIAXIN® XL Filmtab®
(clarithromycin extended-release tablets)
BIAXIN® Granules
(clarithromycin for oral suspension, USP)

To reduce the development of drug-resistant bacteria and maintain the effectiveness of BIAXIN and other antibacterial drugs, BIAXIN should be used only to treat or prevent infections that are proven or strongly suspected to be caused by bacteria.

DESCRIPTION

Clarithromycin is a semi-synthetic macrolide antibiotic. Chemically, it is 6-0-methylerythromycin. The molecular formula is C38H69NO13, and the molecular weight is 747.96. The structural formula is:

Clarithromycin is a white to off-white crystalline powder. It is soluble in acetone, slightly soluble in methanol, ethanol, and acetonitrile, and practically insoluble in water.

BIAXIN is available as immediate-release tablets, extended-release tablets, and granules for oral suspension.

Each yellow oval film-coated immediate-release BIAXIN tablet (clarithromycin tablets, USP) contains 250 mg or 500 mg of clarithromycin and the following inactive ingredients:

250 mg tablets: hypromellose, hydroxypropyl cellulose, croscarmellose sodium, D&C Yellow No. 10, FD&C Blue No. 1, magnesium stearate, microcrystalline cellulose, povidone, pregelatinized starch, propylene glycol, silicon dioxide, sorbic acid, sorbitan monooleate, stearic acid, talc, titanium dioxide, and vanillin.

500 mg tablets: hypromellose, hydroxypropyl cellulose, colloidal silicon dioxide, croscarmellose sodium, D&C Yellow No. 10, magnesium stearate, microcrystalline cellulose, povidone, propylene glycol, sorbic acid, sorbitan monooleate, titanium dioxide, and vanillin.

Each yellow oval film-coated BIAXIN XL tablet (clarithromycin extended-release tablets) contains 500 mg of clarithromycin and the following inactive ingredients: cellulosic polymers, D&C Yellow No. 10, lactose monohydrate, magnesium stearate, propylene glycol, sorbic acid, sorbitan monooleate, talc, titanium dioxide, and vanillin.

After constitution, each 5 mL of BIAXIN suspension (clarithromycin for oral suspension, USP) contains 125 mg or 250 mg of clarithromycin. Each bottle of BIAXIN granules contains 1250 mg (50 mL size), 2500 mg (50 and 100 mL sizes) or 5000 mg (100 mL size) of clarithromycin and the following inactive ingredients: carbomer, castor oil, citric acid, hypromellose phthalate, maltodextrin, potassium sorbate, povidone, silicon dioxide, sucrose, xanthan gum, titanium dioxide and fruit punch flavor.

CLINICAL PHARMACOLOGY

Pharmacokinetics

Clarithromycin is rapidly absorbed from the gastrointestinal tract after oral administration. The absolute bioavailability of 250 mg clarithromycin tablets was approximately 50%. For a single 500 mg dose of clarithromycin, food slightly delays the onset of clarithromycin absorption, increasing the peak time from approximately 2 to 2.5 hours. Food also increases the clarithromycin peak plasma concentration by about 24%, but does not affect the extent of clarithromycin bioavailability. Food does not affect the onset of formation of the antimicrobially active metabolite, 14-OH clarithromycin or its peak plasma concentration but does slightly decrease the extent of metabolite formation, indicated by an 11% decrease in area under the plasma concentration-time curve (AUC). Therefore, BIAXIN tablets may be given without regard to food.

In nonfasting healthy human subjects (males and females), peak plasma concentrations were attained within 2 to 3 hours after oral dosing. Steady-state peak plasma clarithromycin concentrations were attained within 3 days and were approximately 1 to 2 µg/mL with a 250 mg dose administered every 12 hours and 3 to 4 µg/mL with a 500 mg dose administered every 8 to 12 hours. The elimination half-life of clarithromycin was about 3 to 4 hours with 250 mg administered every 12 hours but increased to 5 to 7 hours with 500 mg administered every 8 to 12 hours. The nonlinearity of clarithromycin pharmacokinetics is slight at the recommended doses of 250 mg and 500 mg administered every 8 to 12 hours. With a 250 mg every 12 hours dosing, the principal metabolite, 14-OH clarithromycin, attains a peak steady-state concentration of about 0.6 µg/mL and has an elimination half-life of 5 to 6 hours. With a 500 mg every 8 to 12 hours dosing, the peak steady-state concentration of 14-OH clarithromycin is slightly higher (up to 1 µg/mL), and its elimination half-life is about 7 to 9 hours. With any of these dosing regimens, the steady-state concentration of this metabolite is generally attained within 3 to 4 days.

After a 250 mg tablet every 12 hours, approximately 20% of the dose is excreted in the urine as clarithromycin, while after a 500 mg tablet every 12 hours, the urinary excretion of clarithromycin is somewhat greater, approximately 30%. In comparison, after an oral dose of 250 mg (125 mg/5 mL) suspension every 12 hours, approximately 40% is excreted in urine as clarithromycin. The renal clearance of clarithromycin is, however, relatively independent of the dose size and approximates the normal glomerular filtration rate. The major metabolite found in urine is 14-OH clarithromycin, which accounts for an additional 10% to 15% of the dose with either a 250 mg or a 500 mg tablet administered every 12 hours.

Steady-state concentrations of clarithromycin and 14-OH clarithromycin observed following administration of 500 mg doses of clarithromycin every 12 hours to adult patients with HIV infection were similar to those observed in healthy volunteers. In adult HIV-infected patients taking 500- or 1000-mg doses of clarithromycin every 12 hours, steady-state clarithromycin Cmax values ranged from 2 to 4 µg/mL and 5 to 10 µg/mL, respectively.

The steady-state concentrations of clarithromycin in subjects with impaired hepatic function did not differ from those in normal subjects; however, the 14-OH clarithromycin concentrations were lower in the hepatically impaired subjects. The decreased formation of 14-OH clarithromycin was at least partially offset by an increase in renal clearance of clarithromycin in the subjects with impaired hepatic function when compared to healthy subjects.

The pharmacokinetics of clarithromycin was also altered in subjects with impaired renal function. (See PRECAUTIONS and DOSAGE AND ADMINISTRATION.)

Clarithromycin and the 14-OH clarithromycin metabolite distribute readily into body tissues and fluids. There are no data available on cerebrospinal fluid penetration. Because of high intracellular concentrations, tissue concentrations are higher than serum concentrations. Examples of tissue and serum concentrations are presented below.

CONCENTRATION (after 250 mg q12h)
Tissue Type | Tissue (µg/g) | Serum (µg/mL)
Tonsil | 1.6 | 0.8
Lung | 8.8 | 1.7

Clarithromycin extended-release tablets provide extended absorption of clarithromycin from the gastrointestinal tract after oral administration. Relative to an equal total daily dose of immediate-release clarithromycin tablets, clarithromycin extended-release tablets provide lower and later steady-state peak plasma concentrations but equivalent 24-hour AUC's for both clarithromycin and its microbiologically-active metabolite, 14-OH clarithromycin. While the extent of formation of 14-OH clarithromycin following administration of BIAXIN XL tablets (2 x 500 mg once daily) is not affected by food, administration under fasting conditions is associated with approximately 30% lower clarithromycin AUC relative to administration with food. Therefore, BIAXIN XL tablets should be taken with food.

Steady-State Clarithromycin Plasma Concentration-Time Profiles

In healthy human subjects, steady-state peak plasma clarithromycin concentrations of approximately 2 to 3 µg/mL were achieved about 5 to 8 hours after oral administration of 2 x 500 mg BIAXIN XL tablets once daily; for 14-OH clarithromycin, steady-state peak plasma concentrations of approximately 0.8 µg/mL were attained about 6 to 9 hours after dosing. Steady-state peak plasma clarithromycin concentrations of approximately 1 to 2 µg/mL were achieved about 5 to 6 hours after oral administration of a single 500 mg BIAXIN XL tablet once daily; for 14-OH clarithromycin, steady-state peak plasma concentrations of approximately 0.6 µg/mL were attained about 6 hours after dosing.

When 250 mg doses of clarithromycin as BIAXIN suspension were administered to fasting healthy adult subjects, peak plasma concentrations were attained around 3 hours after dosing. Steady-state peak plasma concentrations were attained in 2 to 3 days and were approximately 2 µg/mL for clarithromycin and 0.7 µg/mL for 14-OH clarithromycin when 250-mg doses of the clarithromycin suspension were administered every 12 hours. Elimination half-life of clarithromycin (3 to 4 hours) and that of 14-OH clarithromycin (5 to 7 hours) were similar to those observed at steady state following administration of equivalent doses of BIAXIN tablets.

For adult patients, the bioavailability of 10 mL of the 125 mg/5 mL suspension or 10 mL of the 250 mg/5 mL suspension is similar to a 250 mg or 500 mg tablet, respectively.

In children requiring antibiotic therapy, administration of 7.5 mg/kg q12h doses of clarithromycin as the suspension generally resulted in steady-state peak plasma concentrations of 3 to 7 µg/mL for clarithromycin and 1 to 2 µg/mL for 14-OH clarithromycin.

In HIV-infected children taking 15 mg/kg every 12 hours, steady-state clarithromycin peak concentrations generally ranged from 6 to 15 µg/mL.

Clarithromycin penetrates into the middle ear fluid of children with secretory otitis media.

CONCENTRATION (after 7.5 mg/kg q12h for 5 doses)
Analyte | Middle Ear Fluid (µg/mL) | Serum (µg/mL)
Clarithromycin | 2.5 | 1.7
14-OH Clarithromycin | 1.3 | 0.8

In adults given 250 mg clarithromycin as suspension (n = 22), food appeared to decrease mean peak plasma clarithromycin concentrations from 1.2 (± 0.4) µg/mL to 1.0 (± 0.4) µg/mL and the extent of absorption from 7.2 (± 2.5) hr• µg/mL to 6.5 (± 3.7) hr• µg/mL.

When children (n = 10) were administered a single oral dose of 7.5 mg/kg suspension, food increased mean peak plasma clarithromycin concentrations from 3.6 (± 1.5) µg/mL to 4.6 (± 2.8) µg/mL and the extent of absorption from 10.0 (± 5.5) hr•µg/mL to 14.2 (± 9.4) hr•µg/mL.

Clarithromycin 500 mg every 8 hours was given in combination with omeprazole 40 mg daily to healthy adult males. The plasma levels of clarithromycin and 14-hydroxy-clarithromycin were increased by the concomitant administration of omeprazole. For clarithromycin, the mean Cmax was 10% greater, the mean Cmin was 27% greater, and the mean AUC0-8 was 15% greater when clarithromycin was administered with omeprazole than when clarithromycin was administered alone. Similar results were seen for 14-hydroxy-clarithromycin, the mean Cmax was 45% greater, the mean Cmin was 57% greater, and the mean AUC0-8 was 45% greater. Clarithromycin concentrations in the gastric tissue and mucus were also increased by concomitant administration of omeprazole.

Clarithromycin Tissue Concentrations 2 hours after Dose (µg/mL)/(µg/g)
Treatment | N | antrum | fundus | N | mucus
Clarithromycin | 5 | 10.48 ± 2.01 | 20.81 ± 7.64 | 4 | 4.15 ± 7.74
Clarithromycin + Omeprazole | 5 | 19.96 ± 4.71 | 24.25 ± 6.37 | 4 | 39.29 ± 32.79

For information about other drugs indicated in combination with BIAXIN, refer to the CLINICAL PHARMACOLOGY section of their package inserts.

Microbiology

Clarithromycin exerts its antibacterial action by binding to the 50S ribosomal subunit of susceptible microorganisms resulting in inhibition of protein synthesis.

Clarithromycin is active in vitro against a variety of aerobic and anaerobic gram-positive and gram-negative microorganisms as well as most Mycobacterium avium complex (MAC) microorganisms.

Additionally, the 14-OH clarithromycin metabolite also has clinically significant antimicrobial activity. The 14-OH clarithromycin is twice as active against Haemophilus influenzae microorganisms as the parent compound. However, for Mycobacterium avium complex (MAC) isolates the 14-OH metabolite is 4 to 7 times less active than clarithromycin. The clinical significance of this activity against Mycobacterium avium complex is unknown.

Clarithromycin has been shown to be active against most strains of the following microorganisms both in vitro and in clinical infections as described in the INDICATIONS AND USAGE section:

Aerobic Gram-positive Microorganisms

Staphylococcus aureus
Streptococcus pneumoniae
Streptococcus pyogenes

Aerobic Gram-negative Microorganisms

Haemophilus influenzae
Haemophilus parainfluenzae
Moraxella catarrhalis

Other Microorganisms

Mycoplasma pneumoniae
Chlamydia pneumoniae (TWAR)

Mycobacteria

Mycobacterium avium complex (MAC) consisting of:
Mycobacterium avium
Mycobacterium intracellulare

Beta-lactamase production should have no effect on clarithromycin activity.

NOTE: Most strains of methicillin-resistant and oxacillin-resistant staphylococci are resistant to clarithromycin.

Omeprazole/clarithromycin dual therapy; ranitidine bismuth citrate/clarithromycin dual therapy; omeprazole/clarithromycin/amoxicillin triple therapy; and lansoprazole/clarithromycin/amoxicillin triple therapy have been shown to be active against most strains of Helicobacter pylori in vitro and in clinical infections as described in the INDICATIONS AND USAGE section.

Helicobacter

Helicobacter pylori

Pretreatment Resistance

Clarithromycin pretreatment resistance rates were 3.5% (4/113) in the omeprazole/clarithromycin dual therapy studies (M93-067, M93-100) and 9.3% (41/439) in the omeprazole/clarithromycin/amoxicillin triple therapy studies (126, 127, M96-446). Clarithromycin pretreatment resistance was 12.6% (44/348) in the ranitidine bismuth citrate/clarithromycin b.i.d. versus t.i.d. clinical study (H2BA3001). Clarithromycin pretreatment resistance rates were 9.5% (91/960) by E-test and 11.3% (12/106) by agar dilution in the lansoprazole/clarithromycin/amoxicillin triple therapy clinical trials (M93-125, M93-130, M93-131, M95-392, and M95-399).

Amoxicillin pretreatment susceptible isolates (< 0.25 µg/mL) were found in 99.3% (436/439) of the patients in the omeprazole/clarithromycin/amoxicillin clinical studies (126, 127, M96-446). Amoxicillin pretreatment minimum inhibitory concentrations (MICs) > 0.25 µg/mL occurred in 0.7% (3/439) of the patients, all of whom were in the clarithromycin/amoxicillin study arm. Amoxicillin pretreatment susceptible isolates (< 0.25 µg/mL) occurred in 97.8% (936/957) and 98.0% (98/100) of the patients in the lansoprazole/clarithromycin/amoxicillin triple-therapy clinical trials by E-test and agar dilution, respectively. Twenty-one of the 957 patients (2.2%) by E-test and 2 of 100 patients (2.0%) by agar dilution had amoxicillin pretreatment MICs of > 0.25 µg/mL. Two patients had an unconfirmed pretreatment amoxicillin minimum inhibitory concentration (MIC) of > 256 µg/mL by E-test.

Clarithromycin Susceptibility Test Results and Clinical/Bacteriological Outcomesa
Clarithromycin Pretreatment Results |  | Clarithromycin Post-treatment Results
 |  | H. pylori negative - eradicated | H. pylori positive - not eradicated Post-treatment susceptibility results
 |  |  | Sb | Ib | Rb | No MIC
Omeprazole 40 mg q.d./clarithromycin 500 mg t.i.d. for 14 days followed by omeprazole 20 mg q.d. for another 14 days (M93-067, M93-100)
Susceptibleb | 108 | 72 | 1 |  | 26 | 9
Intermediateb | 1 |  |  |  | 1
Resistantb | 4 |  |  |  | 4
Ranitidine bismuth citrate 400 mg b.i.d./clarithromycin 500 mg t.i.d. for 14 days followed by ranitidine bismuth citrate 400 mg b.i.d. for another 14 days (H2BA3001)
Susceptibleb | 124 | 98 | 4 |  | 14 | 8
Intermediateb | 3 | 2 |  |  |  | 1
Resistantb | 17 | 1 |  |  | 15 | 1
Ranitidine bismuth citrate 400 mg b.i.d./clarithromycin 500 mg b.i.d. for 14 days followed by ranitidine bismuth citrate 400 mg b.i.d. for another 14 days (H2BA3001)
Susceptible | 125 | 106 | 1 | 1 | 12 | 5
Intermediateb | 2 | 2
Resistantb | 20 | 1 |  |  | 19
Omeprazole 20 mg b.i.d./clarithromycin 500 mg b.i.d./amoxicillin 1 g b.i.d. for 10 days (126, 127, M96-446)
Susceptibleb | 171 | 153 | 7 |  | 3 | 8
Intermediateb
Resistantb | 14 | 4 | 1 |  | 6 | 3
Lansoprazole 30 mg b.i.d./clarithromycin 500 mg b.i.d./amoxicillin 1 g b.i.d. for 14 days (M95-399, M93-131, M95-392)
Susceptibleb | 112 | 105 |  |  |  | 7
Intermediateb | 3 | 3
Resistantb | 17 | 6 |  |  | 7 | 4
Lansoprazole 30 mg b.i.d./clarithromycin 500 mg b.i.d./amoxicillin 1 g b.i.d. for 10 days (M95-399)
Susceptibleb | 42 | 40 | 1 |  | 1
Intermediateb
Resistantb | 4 | 1 |  |  | 3
a Includes only patients with pretreatment clarithromycin susceptibility tests
b Susceptible (S) MIC < 0.25 µg/mL, Intermediate (I) MIC 0.5-1.0 µg/mL, Resistant (R) MIC > 2 µg/mL

Patients not eradicated of H. pylori following omeprazole/clarithromycin, ranitidine bismuth citrate/clarithromycin, omeprazole/clarithromycin/amoxicillin, or lansoprazole/clarithromycin/ amoxicillin therapy would likely have clarithromycin resistant H. pylori isolates. Therefore, for patients who fail therapy, clarithromycin susceptibility testing should be done, if possible. Patients with clarithromycin resistant H. pylori should not be treated with any of the following: omeprazole/clarithromycin dual therapy; ranitidine bismuth citrate/clarithromycin dual therapy; omeprazole/clarithromycin/amoxicillin triple therapy; lansoprazole/clarithromycin/amoxicillin triple therapy; or other regimens which include clarithromycin as the sole antimicrobial agent.

Amoxicillin Susceptibility Test Results and Clinical/Bacteriological Outcomes

In the omeprazole/clarithromycin/amoxicillin triple-therapy clinical trials, 84.9% (157/185) of the patients who had pretreatment amoxicillin susceptible MICs (< 0.25 µg/mL) were eradicated of H. pylori and 15.1% (28/185) failed therapy. Of the 28 patients who failed triple therapy, 11 had no post-treatment susceptibility test results, and 17 had post-treatment H. pylori isolates with amoxicillin susceptible MICs. Eleven of the patients who failed triple therapy also had post-treatment H. pylori isolates with clarithromycin resistant MICs.

In the lansoprazole/clarithromycin/amoxicillin triple-therapy clinical trials, 82.6% (195/236) of the patients that had pretreatment amoxicillin susceptible MICs (< 0.25 µg/mL) were eradicated of H. pylori. Of those with pretreatment amoxicillin MICs of > 0.25 µg/mL, three of six had the H. pylori eradicated. A total of 12.8% (22/172) of the patients failed the 10- and 14-day triple-therapy regimens. Post-treatment susceptibility results were not obtained on 11 of the patients who failed therapy. Nine of the 11 patients with amoxicillin post-treatment MICs that failed the triple-therapy regimen also had clarithromycin resistant H. pylori isolates.

The following in vitro data are available, but their clinical significance is unknown. Clarithromycin exhibits in vitro activity against most strains of the following microorganisms; however, the safety and effectiveness of clarithromycin in treating clinical infections due to these microorganisms have not been established in adequate and well-controlled clinical trials.

Aerobic Gram-positive Microorganisms

Streptococcus agalactiae
Streptococci (Groups C, F, G)
Viridans group streptococci

Aerobic Gram-negative Microorganisms

Bordetella pertussis
Legionella pneumophila
Pasteurella multocida

Anaerobic Gram-positive Microorganisms

Clostridium perfringens
Peptococcus niger
Propionibacterium acnes

Anaerobic Gram-negative Microorganisms

Prevotella melaninogenica (formerly Bacteriodes melaninogenicus)

Susceptibility Testing Excluding Mycobacteria and Helicobacter

Dilution Techniques

Quantitative methods are used to determine antimicrobial minimum inhibitory concentrations (MICs). These MICs provide estimates of the susceptibility of bacteria to antimicrobial compounds. The MICs should be determined using a standardized procedure. Standardized procedures are based on a dilution method^1 (broth or agar) or equivalent with standardized inoculum concentrations and standardized concentrations of clarithromycin powder. The MIC values should be interpreted according to the following criteria:

For testing Staphylococcus spp.
MIC (µg/mL) | Interpretation
≤ 2.0 | Susceptible (S)
4.0 | Intermediate (I)
≥ 8.0 | Resistant (R)

For testing Streptococcus spp. including Streptococcus pneumoniae a
MIC (µg/mL) | Interpretation
≤ 0.25 | Susceptible (S)
0.5 | Intermediate (I)
≥ 1.0 | Resistant (R)
a These interpretive standards are applicable only to broth microdilution susceptibility tests using cation-adjusted Mueller-Hinton broth with 2-5% lysed horse blood.

For testing Haemophilus spp.b
MIC (µg/mL) | Interpretation
≤ 8.0 | Susceptible (S)
16.0 | Intermediate (I)
≥ 32.0 | Resistant (R)
b These interpretive standards are applicable only to broth microdilution susceptibility tests with Haemophilus spp. using Haemophilus Testing Medium (HTM).^1

Note: When testing Streptococcus spp., including Streptococcus pneumoniae, susceptibility and resistance to clarithromycin can be predicted using erythromycin.

A report of "Susceptible" indicates that the pathogen is likely to be inhibited if the antimicrobial compound in the blood reaches the concentrations usually achievable. A report of "Intermediate" indicates that the result should be considered equivocal, and, if the microorganism is not fully susceptible to alternative, clinically feasible drugs, the test should be repeated. This category implies possible clinical applicability in body sites where the drug is physiologically concentrated or in situations where high dosage of drug can be used. This category also provides a buffer zone which prevents small uncontrolled technical factors from causing major discrepancies in interpretation. A report of "Resistant" indicates that the pathogen is not likely to be inhibited if the antimicrobial compound in the blood reaches the concentrations usually achievable; other therapy should be selected.

Standardized susceptibility test procedures require the use of laboratory control microorganisms to control the technical aspects of the laboratory procedures. Standard clarithromycin powder should provide the following MIC values:

Microorganism |  | MIC (µg/mL)
S. aureus | ATCC 29213 | 0.12 to 0.5
S. pneumoniaec | ATCC 49619 | 0.03 to 0.12
Haemophilus influenzaed | ATCC 49247 | 4 to 16
c This quality control range is applicable only to S. pneumoniae ATCC 49619 tested by a microdilution procedure using cation-adjusted Mueller-Hinton broth with 2-5% lysed horse blood.
d This quality control range is applicable only to H. influenzae ATCC 49247 tested by a microdilution procedure using HTM^1.

Diffusion Techniques

Quantitative methods that require measurement of zone diameters also provide reproducible estimates of the susceptibility of bacteria to antimicrobial compounds. One such standardized procedure^2 requires the use of standardized inoculum concentrations. This procedure uses paper disks impregnated with 15-µg clarithromycin to test the susceptibility of microorganisms to clarithromycin.

Reports from the laboratory providing results of the standard single-disk susceptibility test with a 15-µg clarithromycin disk should be interpreted according to the following criteria:

For testing Staphylococcus spp.
Zone diameter (mm) | Interpretation
≥ 18 | Susceptible (S)
14 to 17 | Intermediate (I)
≤ 13 | Resistant (R)

For testing Streptococcus spp. including Streptococcus pneumoniaee
Zone diameter (mm) | Interpretation
≥ 21 | Susceptible (S)
17 to 20 | Intermediate (I)
≤ 16 | Resistant (R)
e These zone diameter standards only apply to tests performed using Mueller-Hinton agar supplemented with 5% sheep blood incubated in 5% CO2.

For testing Haemophilus spp.f
Zone diameter (mm) | Interpretation
≥ 13 | Susceptible (S)
11 to 12 | Intermediate (I)
≤ 10 | Resistant (R)
f These zone diameter standards are applicable only to tests with Haemophilus spp. using HTM^2.

Note: When testing Streptococcus spp., including Streptococcus pneumoniae, susceptibility and resistance to clarithromycin can be predicted using erythromycin.

Interpretation should be as stated above for results using dilution techniques. Interpretation involves correlation of the diameter obtained in the disk test with the MIC for clarithromycin.

As with standardized dilution techniques, diffusion methods require the use of laboratory control microorganisms that are used to control the technical aspects of the laboratory procedures. For the diffusion technique, the 15-µg clarithromycin disk should provide the following zone diameters in this laboratory test quality control strain:

Microorganism |  | Zone diameter (mm)
S. aureus | ATCC 25923 | 26 to 32
S. pneumoniaeg | ATCC 49619 | 25 to 31
Haemophilus influenzaeh | ATCC 49247 | 11 to 17
g This quality control range is applicable only to tests performed by disk diffusion using Mueller-Hinton agar supplemented with 5% defibrinated sheep blood.
h This quality control limit applies to tests conducted with Haemophilus influenzae ATCC 49247 using HTM^2.

In vitro Activity of Clarithromycin against Mycobacteria

Clarithromycin has demonstrated in vitro activity against Mycobacterium avium complex (MAC) microorganisms isolated from both AIDS and non-AIDS patients. While gene probe techniques may be used to distinguish M. avium species from M. intracellulare, many studies only reported results on M. avium complex (MAC) isolates.

Various in vitro methodologies employing broth or solid media at different pH's, with and without oleic acid-albumin-dextrose-catalase (OADC), have been used to determine clarithromycin MIC values for mycobacterial species. In general, MIC values decrease more than 16-fold as the pH of Middlebrook 7H12 broth media increases from 5.0 to 7.4. At pH 7.4, MIC values determined with Mueller-Hinton agar were 4- to 8-fold higher than those observed with Middlebrook 7H12 media. Utilization of oleic acid-albumin-dextrose-catalase (OADC) in these assays has been shown to further alter MIC values.

Clarithromycin activity against 80 MAC isolates from AIDS patients and 211 MAC isolates from non-AIDS patients was evaluated using a microdilution method with Middlebrook 7H9 broth. Results showed an MIC value of ≤ 4.0 µg/mL in 81% and 89% of the AIDS and non-AIDS MAC isolates, respectively. Twelve percent of the non-AIDS isolates had an MIC value ≤ 0.5 µg/mL. Clarithromycin was also shown to be active against phagocytized M. avium complex (MAC) in mouse and human macrophage cell cultures as well as in the beige mouse infection model.

Clarithromycin activity was evaluated against Mycobacterium tuberculosis microorganisms. In one study utilizing the agar dilution method with Middlebrook 7H10 media, 3 of 30 clinical isolates had an MIC of 2.5 µg/mL. Clarithromycin inhibited all isolates at > 10.0 µg/mL.

Susceptibility Testing for Mycobacterium avium Complex (MAC)

The disk diffusion and dilution techniques for susceptibility testing against gram-positive and gram-negative bacteria should not be used for determining clarithromycin MIC values against mycobacteria. In vitro susceptibility testing methods and diagnostic products currently available for determining minimum inhibitory concentration (MIC) values against Mycobacterium avium complex (MAC) organisms have not been standardized or validated. Clarithromycin MIC values will vary depending on the susceptibility testing method employed, composition and pH of the media, and the utilization of nutritional supplements. Breakpoints to determine whether clinical isolates of M. avium or M. intracellulare are susceptible or resistant to clarithromycin have not been established.

Susceptibility Test for Helicobacter pylori

The reference methodology for susceptibility testing of H. pylori is agar dilution MICs.^3 One to three microliters of an inoculum equivalent to a No. 2 McFarland standard (1 x 10^7-1 x 10^8 CFU/mL for H. pylori) are inoculated directly onto freshly prepared antimicrobial containing Mueller-Hinton agar plates with 5% aged defibrinated sheep blood (> 2-weeks old). The agar dilution plates are incubated at 35°C in a microaerobic environment produced by a gas generating system suitable for Campylobacter species. After 3 days of incubation, the MICs are recorded as the lowest concentration of antimicrobial agent required to inhibit growth of the organism. The clarithromycin and amoxicillin MIC values should be interpreted according to the following criteria:

Clarithromycin MIC (µg/mL) i | Interpretation
< 0.25 | Susceptible (S)
0.5-1.0 | Intermediate (I)
> 2.0 | Resistant (R)

Amoxicillin MIC (µg/mL) i,j | Interpretation
< 0.25 | Susceptible (S)
i These are tentative breakpoints for the agar dilution methodology, and they should not be used to interpret results obtained using alternative methods.
j There were not enough organisms with MICs > 0.25 µg/mL to determine a resistance breakpoint.

Standardized susceptibility test procedures require the use of laboratory control microorganisms to control the technical aspects of the laboratory procedures. Standard clarithromycin and amoxicillin powders should provide the following MIC values:

Microorganisms |  | Antimicrobial Agent | MIC (µg/mL)k
H. pylori | ATCC 43504 | Clarithromycin | 0.015-0.12 µg/mL
H. pylori | ATCC 43504 | Amoxicillin | 0.015-0.12 µg/mL
k These are quality control ranges for the agar dilution methodology and they should not be used to control test results obtained using alternative methods.

INDICATIONS AND USAGE

BIAXIN Filmtab (clarithromycin tablets, USP) and BIAXIN Granules (clarithromycin for oral suspension, USP) are indicated for the treatment of mild to moderate infections caused by susceptible strains of the designated microorganisms in the conditions as listed below:

Adults (BIAXIN Filmtab Tablets and Granules for Oral Suspension)

Pharyngitis/Tonsillitis due to Streptococcus pyogenes (The usual drug of choice in the treatment and prevention of streptococcal infections and the prophylaxis of rheumatic fever is penicillin administered by either the intramuscular or the oral route. Clarithromycin is generally effective in the eradication of S. pyogenes from the nasopharynx; however, data establishing the efficacy of clarithromycin in the subsequent prevention of rheumatic fever are not available at present).

Acute maxillary sinusitis due to Haemophilus influenzae, Moraxella catarrhalis, or Streptococcus pneumoniae.

Acute bacterial exacerbation of chronic bronchitis due to Haemophilus influenzae , Haemophilus parainfluenzae, Moraxella catarrhalis, or Streptococcus pneumoniae.

Community-Acquired Pneumonia due to Haemophilus influenzae, Mycoplasma pneumoniae, Streptococcus pneumoniae, or Chlamydia pneumoniae (TWAR).

Uncomplicated skin and skin structure infections due to Staphylococcus aureus , or Streptococcus pyogenes (Abscesses usually require surgical drainage).

Disseminated mycobacterial infections due to Mycobacterium avium, or Mycobacterium intracellulare

BIAXIN (clarithromycin) Filmtab tablets in combination with amoxicillin and PREVACID (lansoprazole) or PRILOSEC (omeprazole) Delayed-Release Capsules, as triple therapy, are indicated for the treatment of patients with H. pylori infection and duodenal ulcer disease (active or five-year history of duodenal ulcer) to eradicate H. pylori.

BIAXIN Filmtab tablets in combination with PRILOSEC (omeprazole) capsules or TRITEC (ranitidine bismuth citrate) tablets are also indicated for the treatment of patients with an active duodenal ulcer associated with H. pylori infection. However, regimens which contain clarithromycin as the single antimicrobial agent are more likely to be associated with the development of clarithromycin resistance among patients who fail therapy. Clarithromycin-containing regimens should not be used in patients with known or suspected clarithromycin resistant isolates because the efficacy of treatment is reduced in this setting.

In patients who fail therapy, susceptibility testing should be done if possible. If resistance to clarithromycin is demonstrated, a non-clarithromycin-containing therapy is recommended. (For information on development of resistance see Microbiology section.) The eradication of H. pylori has been demonstrated to reduce the risk of duodenal ulcer recurrence.

Children (BIAXIN Filmtab Tablets and Granules for Oral Suspension)

Pharyngitis/Tonsillitis due to Streptococcus pyogenes.

Community-Acquired Pneumonia due to Mycoplasma pneumoniae, Streptococcus pneumoniae, or Chlamydia pneumoniae (TWAR)

Acute maxillary sinusitis due to Haemophilus influenzae, Moraxella catarrhalis, or Streptococcus pneumoniae

Acute otitis media due to Haemophilus influenzae, Moraxella catarrhalis, or Streptococcus pneumoniae

NOTE: For information on otitis media, see CLINICAL STUDIES - Otitis Media.

Uncomplicated skin and skin structure infections due to Staphylococcus aureus, or Streptococcus pyogenes (Abscesses usually require surgical drainage.)

Disseminated mycobacterial infections due to Mycobacterium avium, or Mycobacterium intracellulare

Adults (BIAXIN XL Filmtab Tablets)

BIAXIN XL Filmtab (clarithromycin extended-release tablets) are indicated for the treatment of adults with mild to moderate infection caused by susceptible strains of the designated microorganisms in the conditions listed below:

Acute maxillary sinusitis due to Haemophilus influenzae, Moraxella catarrhalis, or Streptococcus pneumoniae

Acute bacterial exacerbation of chronic bronchitis due to Haemophilus influenzae, Haemophilus parainfluenzae, Moraxella catarrhalis, or Streptococcus pneumoniae

Community-Acquired Pneumonia due to Haemophilus influenzae, Haemophilus parainfluenzae, Moraxella catarrhalis, Streptococcus pneumoniae, Chlamydia pneumoniae (TWAR), or Mycoplasma pneumoniae

THE EFFICACY AND SAFETY OF BIAXIN XL IN TREATING OTHER INFECTIONS FOR WHICH OTHER FORMULATIONS OF BIAXIN ARE APPROVED HAVE NOT BEEN ESTABLISHED.

Prophylaxis

BIAXIN Filmtab tablets and BIAXIN Granules for oral suspension are indicated for the prevention of disseminated Mycobacterium avium complex (MAC) disease in patients with advanced HIV infection.

To reduce the development of drug-resistant bacteria and maintain the effectiveness of BIAXIN and other antibacterial drugs, BIAXIN should be used only to treat or prevent infections that are proven or strongly suspected to be caused by susceptible bacteria. When culture and susceptibility information are available, they should be considered in selecting or modifying antibacterial therapy. In the absence of such data, local epidemiology and susceptibility patterns may contribute to the empiric selection of therapy.

CONTRAINDICATIONS

Clarithromycin is contraindicated in patients with a known hypersensitivity to clarithromycin or any of its excipients, erythromycin, or any of the macrolide antibiotics.

Clarithromycin is contraindicated in patients with a history of cholestatic jaundice/hepatic dysfunction associated with prior use of clarithromycin.

Concomitant administration of clarithromycin and any of the following drugs is contraindicated: cisapride, pimozide, astemizole, terfenadine, and ergotamine or dihydroergotamine (see Drug Interactions). There have been post-marketing reports of drug interactions when clarithromycin and/or erythromycin are coadministered with cisapride, pimozide, astemizole, or terfenadine resulting in cardiac arrhythmias (QT prolongation, ventricular tachycardia, ventricular fibrillation, and torsades de pointes) most likely due to inhibition of metabolism of these drugs by erythromycin and clarithromycin. Fatalities have been reported.

Concomitant administration of clarithromycin and colchicine is contraindicated in patients with renal or hepatic impairment.

Clarithromycin should not be given to patients with history of QT prolongation or ventricular cardiac arrhythmia, including torsades de pointes.

Clarithromycin should not be used concomitantly with HMG-CoA reductase inhibitors (statins), lovastatin or simvastatin, due to the risk of rhabdomyolysis. Treatment with these agents should be discontinued during clarithromycin treatment (see WARNINGS).

For information about contraindications of other drugs indicated in combination with BIAXIN, refer to the CONTRAINDICATIONS section of their package inserts.

WARNINGS

Use In Pregnancy

CLARITHROMYCIN SHOULD NOT BE USED IN PREGNANT WOMEN EXCEPT IN CLINICAL CIRCUMSTANCES WHERE NO ALTERNATIVE THERAPY IS APPROPRIATE. IF PREGNANCY OCCURS WHILE TAKING THIS DRUG, THE PATIENT SHOULD BE APPRISED OF THE POTENTIAL HAZARD TO THE FETUS. CLARITHROMYCIN HAS DEMONSTRATED ADVERSE EFFECTS OF PREGNANCY OUTCOME AND/OR EMBRYO-FETAL DEVELOPMENT IN MONKEYS, RATS, MICE, AND RABBITS AT DOSES THAT PRODUCED PLASMA LEVELS 2 TO 17 TIMES THE SERUM LEVELS ACHIEVED IN HUMANS TREATED AT THE MAXIMUM RECOMMENDED HUMAN DOSES. (See PRECAUTIONS - Pregnancy.)

Hepatotoxicity

Hepatic dysfunction, including increased liver enzymes, and hepatocellular and/or cholestatic hepatitis, with or without jaundice, has been reported with clarithromycin. This hepatic dysfunction may be severe and is usually reversible. In some instances, hepatic failure with fatal outcome has been reported and generally has been associated with serious underlying diseases and/or concomitant medications. Discontinue clarithromycin immediately if signs and symptoms of hepatitis occur.

Drug Interactions

Serious adverse reactions have been reported in patients taking clarithromycin concomitantly with CYP3A4 substrates. These include colchicine toxicity with colchicine; rhabdomyolysis with simvastatin, lovastatin, and atorvastatin; and hypotension with calcium channel blockers metabolized by CYP3A4 (e.g., verapamil, amlodipine, diltiazem) (see CONTRAINDICATIONS and PRECAUTIONS – Drug Interactions).

Life-threatening and fatal drug interactions have been reported in patients treated with clarithromycin and colchicine. Clarithromycin is a strong CYP3A4 inhibitor and this interaction may occur while using both drugs at their recommended doses. If co-administration of clarithromycin and colchicine is necessary in patients with normal renal and hepatic function, the dose of colchicine should be reduced. Patients should be monitored for clinical symptoms of colchicine toxicity. Concomitant administration of clarithromycin and colchicine is contraindicated in patients with renal or hepatic impairment (see CONTRAINDICATIONS and PRECAUTIONS – Drug Interactions).

Clostridium difficile associated diarrhea (CDAD) has been reported with use of nearly all antibacterial agents, including BIAXIN, and may range in severity from mild diarrhea to fatal colitis. Treatment with antibacterial agents alters the normal flora of the colon leading to overgrowth of C. difficile.

C. difficile produces toxins A and B which contribute to the development of CDAD. Hypertoxin producing strains of C. difficile cause increased morbidity and mortality, as these infections can be refractory to antimicrobial therapy and may require colectomy. CDAD must be considered in all patients who present with diarrhea following antibiotic use. Careful medical history is necessary since CDAD has been reported to occur over two months after the administration of antibacterial agents.

If CDAD is suspected or confirmed, ongoing antibiotic use not directed against C. difficile may need to be discontinued. Appropriate fluid and electrolyte management, protein supplementation, antibiotic treatment of C. difficile, and surgical evaluation should be instituted as clinically indicated.

For information about warnings of other drugs indicated in combination with BIAXIN, refer to the WARNINGS section of their package inserts.

Due to the risk for QT prolongation clarithromycin should be used with caution in patients with a medical condition associated with an increased tendency toward QT prolongation and torsades de pointes.

In the event of severe acute hypersensitivity reactions, such as anaphylaxis, Stevens-Johnson Syndrome, toxic epidermal necrolysis, drug rash with eosinophilia and systemic symptoms (DRESS), and Henoch-Schonlein purpura clarithromycin therapy should be discontinued immediately and appropriate treatment should be urgently initiated.

Oral Hypoglycemic Agents/Insulin

The concomitant use of clarithromycin and oral hypoglycemic agents and/or insulin can result in significant hypoglycemia. With certain hypoglycemic drugs such as nateglinide, pioglitazone, repaglinide and rosiglitazone, inhibition of CYP3A enzyme by clarithromycin may be involved and could cause hypolgycemia when used concomitantly. Careful monitoring of glucose is recommended.

Oral Anticoagulants

There is a risk of serious hemorrhage and significant elevations in INR and prothrombin time when clarithromycin is co-administered with warfarin. INR and prothrombin times should be frequently monitored while patients are receiving clarithromycin and oral anticoagulants concurrently.

HMG-CoA Reductase Inhibitors

Concomitant use of clarithromycin with lovastatin or simvastatin is contraindicated (see CONTRAINDICATIONS). As with other macrolides, clarithromycin has been reported to increase concentrations of HMG-CoA reductase inhibitors. Rare reports of rhabdomyolysis have been reported in patients taking these drugs concomitantly. Patients should be monitored for signs and symptoms of myopathy.

Rare reports of rhabdomyolysis have also been reported in patients taking atorvastatin or rosuvastatin concomitantly with clarithromycin. When used with clarithromycin, atorvastatin or rosuvastatin should be administered in the lowest possible doses. Adjustment of the statin dose or use of a statin that is not dependent on CYP3A metabolism (e.g.fluvastatin or pravastatin) should be considered.

PRECAUTIONS

General

Prescribing BIAXIN in the absence of a proven or strongly suspected bacterial infection or a prophylactic indication is unlikely to provide benefit to the patient and increases the risk of the development of drug-resistant bacteria.

Clarithromycin is principally excreted via the liver and kidney. Clarithromycin may be administered without dosage adjustment to patients with hepatic impairment and normal renal function. However, in the presence of severe renal impairment with or without coexisting hepatic impairment, decreased dosage or prolonged dosing intervals may be appropriate.

Clarithromycin in combination with ranitidine bismuth citrate therapy is not recommended in patients with creatinine clearance less than 25 mL/min. (See DOSAGE AND ADMINISTRATION.)

Clarithromycin in combination with ranitidine bismuth citrate should not be used in patients with a history of acute porphyria.

Exacerbation of symptoms of myasthenia gravis and new onset of symptoms of myasthenic syndrome has been reported in patients receiving clarithromycin therapy.

For information about precautions of other drugs indicated in combination with BIAXIN, refer to the PRECAUTIONS section of their package inserts.

Information to Patients

Patients should be counseled that antibacterial drugs including BIAXIN should only be used to treat bacterial infections. They do not treat viral infections (e.g., the common cold). When BIAXIN is prescribed to treat a bacterial infection, patients should be told that although it is common to feel better early in the course of therapy, the medication should be taken exactly as directed. Skipping doses or not completing the full course of therapy may (1) decrease the effectiveness of the immediate treatment and (2) increase the likelihood that bacteria will develop resistance and will not be treatable by BIAXIN or other antibacterial drugs in the future.

Diarrhea is a common problem caused by antibiotics which usually ends when the antibiotic is discontinued. Sometimes after starting treatment with antibiotics, patients can develop watery and bloody stools (with or without stomach cramps and fever) even as late as two or more months after having taken the last dose of the antibiotic. If this occurs, patients should contact their physician as soon as possible.

BIAXIN may interact with some drugs; therefore patients should be advised to report to their doctor the use of any other medications.

BIAXIN tablets and oral suspension can be taken with or without food and can be taken with milk; however, BIAXIN XL tablets should be taken with food. Do NOT refrigerate the suspension.

Drug Interactions

Clarithromycin use in patients who are receiving theophylline may be associated with an increase of serum theophylline concentrations. Monitoring of serum theophylline concentrations should be considered for patients receiving high doses of theophylline or with baseline concentrations in the upper therapeutic range. In two studies in which theophylline was administered with clarithromycin (a theophylline sustained-release formulation was dosed at either 6.5 mg/kg or 12 mg/kg together with 250 or 500 mg q12h clarithromycin), the steady-state levels of Cmax, Cmin, and the area under the serum concentration time curve (AUC) of theophylline increased about 20%.

Hypotension, bradyarrhythmias, and lactic acidosis have been observed in patients receiving concurrent verapamil, belonging to the calcium channel blockers drug class.

Concomitant administration of single doses of clarithromycin and carbamazepine has been shown to result in increased plasma concentrations of carbamazepine. Blood level monitoring of carbamazepine may be considered.

When clarithromycin and terfenadine were coadministered, plasma concentrations of the active acid metabolite of terfenadine were threefold higher, on average, than the values observed when terfenadine was administered alone. The pharmacokinetics of clarithromycin and the 14-OH-clarithromycin were not significantly affected by coadministration of terfenadine once clarithromycin reached steady-state conditions. Concomitant administration of clarithromycin with terfenadine is contraindicated. (See CONTRAINDICATIONS.)

Clarithromycin 500 mg every 8 hours was given in combination with omeprazole 40 mg daily to healthy adult subjects. The steady-state plasma concentrations of omeprazole were increased (Cmax, AUC0-24, and t½ increases of 30%, 89%, and 34%, respectively), by the concomitant administration of clarithromycin. The mean 24-hour gastric pH value was 5.2 when omeprazole was administered alone and 5.7 when coadministered with clarithromycin.

Coadministration of clarithromycin with ranitidine bismuth citrate resulted in increased plasma ranitidine concentrations (57%), increased plasma bismuth trough concentrations (48%), and increased 14-hydroxy-clarithromycin plasma concentrations (31%). These effects are clinically insignificant.

Simultaneous oral administration of BIAXIN tablets and zidovudine to HIV-infected adult patients may result in decreased steady-state zidovudine concentrations. Following administration of clarithromycin 500 mg tablets twice daily with zidovudine 100 mg every 4 hours, the steady-state zidovudine AUC decreased 12% compared to administration of zidovudine alone (n=4). Individual values ranged from a decrease of 34% to an increase of 14%. When clarithromycin tablets were administered two to four hours prior to zidovudine, the steady-state zidovudine Cmax increased 100% whereas the AUC was unaffected (n=24). Administration of clarithromycin and zidovudine should be separated by at least two hours. The impact of co-administration of clarithromycin extended-release tablets and zidovudine has not been evaluated.

Simultaneous administration of BIAXIN tablets and didanosine to 12 HIV-infected adult patients resulted in no statistically significant change in didanosine pharmacokinetics.

Following administration of fluconazole 200 mg daily and clarithromycin 500 mg twice daily to 21 healthy volunteers, the steady-state clarithromycin Cmin and AUC increased 33% and 18%, respectively. Steady-state concentrations of 14-OH clarithromycin were not significantly affected by concomitant administration of fluconazole. No dosage adjustment of clarithromycin is necessary when co-administered with fluconazole.

Ritonavir

Concomitant administration of clarithromycin and ritonavir (n = 22) resulted in a 77% increase in clarithromycin AUC and a 100% decrease in the AUC of 14-OH clarithromycin. Clarithromycin may be administered without dosage adjustment to patients with normal renal function taking ritonavir. Since concentrations of 14-OH clarithromycin are significantly reduced when clarithromycin is co-administered with ritonavir, alternative antibacterial therapy should be considered for indications other than infections due to Mycobacterium avium complex (see PRECAUTIONS – Drug Interactions). Doses of clarithromycin greater than 1000 mg per day should not be co-administered with protease inhibitors.

Spontaneous reports in the post-marketing period suggest that concomitant administration of clarithromycin and oral anticoagulants may potentiate the effects of the oral anticoagulants. Prothrombin times should be carefully monitored while patients are receiving clarithromycin and oral anticoagulants simultaneously.

Digoxin is a substrate for P-glycoprotein (Pgp) and clarithromycin is known to inhibit Pgp. When clarithromycin and digoxin are co-administered, inhibition of Pgp by clarithromycin may lead to increased exposure of digoxin. Elevated digoxin serum concentrations in patients receiving clarithromycin and digoxin concomitantly have been reported in post-marketing surveillance. Some patients have shown clinical signs consistent with digoxin toxicity, including potentially fatal arrhythmias. Monitoring of serum digoxin concentrations should be considered, especially for patients with digoxin concentrations in the upper therapeutic range.

Co-administration of clarithromycin, known to inhibit CYP3A, and a drug primarily metabolized by CYP3A may be associated with elevations in drug concentrations that could increase or prolong both therapeutic and adverse effects of the concomitant drug.

Clarithromycin should be used with caution in patients receiving treatment with other drugs known to be CYP3A enzyme substrates, especially if the CYP3A substrate has a narrow safety margin (e.g., carbamazepine) and/or the substrate is extensively metabolized by this enzyme. Dosage adjustments may be considered, and when possible, serum concentrations of drugs primarily metabolized by CYP3A should be monitored closely in patients concurrently receiving clarithromycin.

The following are examples of some clinically significant CYP3A based drug interactions. Interactions with other drugs metabolized by the CYP3A isoform are also possible.

Carbamazepine and Terfenadine

Increased serum concentrations of carbamazepine and the active acid metabolite of terfenadine were observed in clinical trials with clarithromycin.

Colchicine

Colchicine is a substrate for both CYP3A and the efflux transporter, P-glycoprotein (Pgp). Clarithromycin and other macrolides are known to inhibit CYP3A and Pgp. When a single dose of colchicine 0.6 mg was administered with clarithromycin 250 mg BID for 7 days, the colchicine Cmax increased 197% and the AUC0-∞ increased 239% compared to administration of colchicine alone. The dose of colchicine should be reduced when co-administered with clarithromycin in patients with normal renal and hepatic function. Concomitant use of clarithromycin and colchicine is contraindicated in patients with renal or hepatic impairment. (See WARNINGS).

Efavirenz, Nevirapine, Rifampicin, Rifabutin, and Rifapentine

Inducers of CYP3A enzymes, such as efavirenz, nevirapine, rifampicin, rifabutin, and rifapentine will increase the metabolism of clarithromycin, thus decreasing plasma concentrations of clarithromycin, while increasing those of 14-OH-clarithromycin. Since the microbiological activities of clarithromycin and 14-OH-clarithromycin are different for different bacteria, the intended therapeutic effect could be impaired during concomitant administration of clarithromycin and enzyme inducers. Alternative antibacterial treatment should be considered when treating patients receiving inducers of CYP3A.

Sildenafil, Tadalafil, and Vardenafil

Each of these phosphodiesterase inhibitors is primarily metabolized by CYP3A, and CYP3A will be inhibited by concomitant administration of clarithromycin. Co-administration of clarithromycin with sildenafil, tadalafil, or vardenafil will result in increased exposure of these phosphodiesterase inhibitors. Co-administration of these phosphodiesterase inhibitors with clarithromycin is not recommended.

Tolterodine

The primary route of metabolism for tolterodine is via CYP2D6. However, in a subset of the population devoid of CYP2D6, the identified pathway of metabolism is via CYP3A. In this population subset, inhibition of CYP3A results in significantly higher serum concentrations of tolterodine. Tolterodine 1 mg twice daily is recommended in patients deficient in CYP2D6 activity (poor metabolizers) when co-administered with clarithromycin.

Triazolobenzodiazepines (e.g., alprazolam, midazolam, triazolam)

When a single dose of midazolam was co-administered with clarithromycin tablets (500 mg twice daily for 7 days), midazolam AUC increased 174% after intravenous administration of midazolam and 600% after oral administration. When oral midazolam is co-administered with clarithromycin, dose adjustments may be necessary and possible prolongation and intensity of effect should be anticipated. Caution and appropriate dose adjustments should be considered when triazolam or alprazolam is co-administered with clarithromycin. For benzodiazepines which are not metabolized by CYP3A (e.g., temazepam, nitrazepam, lorazepam), a clinically important interaction with clarithromycin is unlikely.

There have been post-marketing reports of drug interactions and central nervous system (CNS) effects (e.g., somnolence and confusion) with the concomitant use of clarithromycin and triazolam. Monitoring the patient for increased CNS pharmacological effects is suggested.

Atazanavir

Both clarithromycin and atazanavir are substrates and inhibitors of CYP3A, and there is evidence of a bi-directional drug interaction. Following administration of clarithromycin (500 mg twice daily) with atazanavir (400 mg once daily), the clarithromycin AUC increased 94%, the 14-OH clarithromycin AUC decreased 70% and the atazanavir AUC increased 28%. When clarithromycin is co-administered with atazanavir, the dose of clarithromycin should be decreased by 50%. Since concentrations of 14-OH clarithromycin are significantly reduced when clarithromycin is co-administered with atazanavir, alternative antibacterial therapy should be considered for indications other than infections due to Mycobacterium avium complex (see PRECAUTIONS – Drug Interactions). Doses of clarithromycin greater than 1000 mg per day should not be co-administered with protease inhibitors.

Itraconazole

Both clarithromycin and itraconazole are substrates and inhibitors of CYP3A, potentially leading to a bi-directional drug interaction when administered concomitantly. Clarithromycin may increase the plasma concentrations of itraconazole, while itraconazole may increase the plasma concentrations of clarithromycin. Patients taking itraconazole and clarithromycin concomitantly should be monitored closely for signs or symptoms of increased or prolonged adverse reactions.

Saquinavir

Both clarithromycin and saquinavir are substrates and inhibitors of CYP3A and there is evidence of a bi-directional drug interaction. Following administration of clarithromycin (500 mg bid) and saquinavir (soft gelatin capsules, 1200 mg tid) to 12 healthy volunteers, the steady-state saquinavir AUC and Cmax increased 177% and 187% respectively compared to administration of saquinavir alone. Clarithromycin AUC and Cmax increased 45% and 39% respectively, whereas the 14–OH clarithromycin AUC and Cmax decreased 24% and 34% respectively, compared to administration with clarithromycin alone. No dose adjustment of clarithromycin is necessary when clarithromycin is co-administered with saquinavir in patients with normal renal function. When saquinavir is co-administered with ritonavir, consideration should be given to the potential effects of ritonavir on clarithromycin (refer to interaction between clarithromycin and ritonavir) (see PRECAUTIONS — Drug Interactions).

The following CYP3A based drug interactions have been observed with erythromycin products and/or with clarithromycin in post-marketing experience:

Antiarrhythmics

There have been post-marketing reports of torsades de pointes occurring with concurrent use of clarithromycin and quinidine or disopyramide. Electrocardiograms should be monitored for QTc prolongation during coadministration of clarithromycin with these drugs. Serum concentrations of these medications should also be monitored.

Ergotamine/Dihydroergotamine

Post-marketing reports indicate that coadministration of clarithromycin with ergotamine or dihydroergotamine has been associated with acute ergot toxicity characterized by vasospasm and ischemia of the extremities and other tissues including the central nervous system. Concomitant administration of clarithromycin with ergotamine or dihydroergotamine is contraindicated (see CONTRAINDICATIONS).

Triazolobenziodidiazepines (Such as Triazolam and Alprazolam) and Related Benzodiazepines (Such as Midazolam)

Erythromycin has been reported to decrease the clearance of triazolam and midazolam, and thus, may increase the pharmacologic effect of these benzodiazepines. There have been post-marketing reports of drug interactions and CNS effects (e.g., somnolence and confusion) with the concomitant use of clarithromycin and triazolam.

Sildenafil (Viagra)

Erythromycin has been reported to increase the systemic exposure (AUC) of sildenafil. A similar interaction may occur with clarithromycin; reduction of sildenafil dosage should be considered. (See Viagra package insert.)

There have been spontaneous or published reports of CYP3A based interactions of erythromycin and/or clarithromycin with cyclosporine, carbamazepine, tacrolimus, alfentanil, disopyramide, rifabutin, quinidine, methylprednisolone, cilostazol, bromocriptine and vinblastine.

Concomitant administration of clarithromycin with cisapride, pimozide, astemizole, or terfenadine is contraindicated (see CONTRAINDICATIONS.)

In addition, there have been reports of interactions of erythromycin or clarithromycin with drugs not thought to be metabolized by CYP3A, including hexobarbital, phenytoin, and valproate.

Carcinogenesis, Mutagenesis, Impairment of Fertility

The following in vitro mutagenicity tests have been conducted with clarithromycin:

Salmonella/Mammalian Microsomes Test

Bacterial Induced Mutation Frequency Test

In Vitro Chromosome Aberration Test

Rat Hepatocyte DNA Synthesis Assay

Mouse Lymphoma Assay

Mouse Dominant Lethal Study

Mouse Micronucleus Test

All tests had negative results except the In Vitro Chromosome Aberration Test which was weakly positive in one test and negative in another.

In addition, a Bacterial Reverse-Mutation Test (Ames Test) has been performed on clarithromycin metabolites with negative results.

Fertility and reproduction studies have shown that daily doses of up to 160 mg/kg/day (1.3 times the recommended maximum human dose based on mg/m^2) to male and female rats caused no adverse effects on the estrous cycle, fertility, parturition, or number and viability of offspring. Plasma levels in rats after 150 mg/kg/day were 2 times the human serum levels.

In the 150 mg/kg/day monkey studies, plasma levels were 3 times the human serum levels. When given orally at 150 mg/kg/day (2.4 times the recommended maximum human dose based on mg/m^2), clarithromycin was shown to produce embryonic loss in monkeys. This effect has been attributed to marked maternal toxicity of the drug at this high dose.

In rabbits, in utero fetal loss occurred at an intravenous dose of 33 mg/m^2, which is 17 times less than the maximum proposed human oral daily dose of 618 mg/m^2.

Long-term studies in animals have not been performed to evaluate the carcinogenic potential of clarithromycin.

Pregnancy

Teratogenic Effects

Pregnancy Category C

Four teratogenicity studies in rats (three with oral doses and one with intravenous doses up to 160 mg/kg/day administered during the period of major organogenesis) and two in rabbits at oral doses up to 125 mg/kg/day (approximately 2 times the recommended maximum human dose based on mg/m^2) or intravenous doses of 30 mg/kg/day administered during gestation days 6 to 18 failed to demonstrate any teratogenicity from clarithromycin. Two additional oral studies in a different rat strain at similar doses and similar conditions demonstrated a low incidence of cardiovascular anomalies at doses of 150 mg/kg/day administered during gestation days 6 to 15. Plasma levels after 150 mg/kg/day were 2 times the human serum levels. Four studies in mice revealed a variable incidence of cleft palate following oral doses of 1000 mg/kg/day (2 and 4 times the recommended maximum human dose based on mg/m^2, respectively) during gestation days 6 to 15. Cleft palate was also seen at 500 mg/kg/day. The 1000 mg/kg/day exposure resulted in plasma levels 17 times the human serum levels. In monkeys, an oral dose of 70 mg/kg/day (an approximate equidose of the recommended maximum human dose based on mg/m^2) produced fetal growth retardation at plasma levels that were 2 times the human serum levels.

There are no adequate and well-controlled studies in pregnant women. Clarithromycin should be used during pregnancy only if the potential benefit justifies the potential risk to the fetus. (See WARNINGS.)

Nursing Mothers

It is not known whether clarithromycin is excreted in human milk. Because many drugs are excreted in human milk, caution should be exercised when clarithromycin is administered to a nursing woman. It is known that clarithromycin is excreted in the milk of lactating animals and that other drugs of this class are excreted in human milk. Preweaned rats, exposed indirectly via consumption of milk from dams treated with 150 mg/kg/day for 3 weeks, were not adversely affected, despite data indicating higher drug levels in milk than in plasma.

Pediatric Use

Safety and effectiveness of clarithromycin in pediatric patients under 6 months of age have not been established. The safety of clarithromycin has not been studied in MAC patients under the age of 20 months. Neonatal and juvenile animals tolerated clarithromycin in a manner similar to adult animals. Young animals were slightly more intolerant to acute overdosage and to subtle reductions in erythrocytes, platelets and leukocytes but were less sensitive to toxicity in the liver, kidney, thymus, and genitalia.

Geriatric Use

In a steady-state study in which healthy elderly subjects (age 65 to 81 years old) were given 500 mg every 12 hours, the maximum serum concentrations and area under the curves of clarithromycin and 14-OH clarithromycin were increased compared to those achieved in healthy young adults. These changes in pharmacokinetics parallel known age-related decreases in renal function. In clinical trials, elderly patients did not have an increased incidence of adverse events when compared to younger patients. Dosage adjustment should be considered in elderly patients with severe renal impairment. (See WARNINGS and PRECAUTIONS.)

ADVERSE REACTIONS

The majority of side effects observed in clinical trials were of a mild and transient nature. Fewer than 3% of adult patients without mycobacterial infections and fewer than 2% of pediatric patients without mycobacterial infections discontinued therapy because of drug-related side effects. Fewer than 2% of adult patients taking BIAXIN XL tablets discontinued therapy because of drug-related side effects.

The most frequently reported events in adults taking BIAXIN tablets (clarithromycin tablets, USP) were diarrhea (3%), nausea (3%), abnormal taste (3%), dyspepsia (2%), abdominal pain/discomfort (2%), and headache (2%). In pediatric patients, the most frequently reported events were diarrhea (6%), vomiting (6%), abdominal pain (3%), rash (3%), and headache (2%). Most of these events were described as mild or moderate in severity. Of the reported adverse events, only 1% was described as severe.

The most frequently reported events in adults taking BIAXIN XL (Clarithromycin extended-release tablets) were diarrhea (6%), abnormal taste (7%), and nausea (3%). Most of these events were described as mild or moderate in severity. Of the reported adverse events, less than 1% were described as severe.

In the acute exacerbation of chronic bronchitis and acute maxillary sinusitis studies overall gastrointestinal adverse events were reported by a similar proportion of patients taking either BIAXIN tablets or BIAXIN XL tablets; however, patients taking BIAXIN XL tablets reported significantly less severe gastrointestinal symptoms compared to patients taking BIAXIN tablets. In addition, patients taking BIAXIN XL tablets had significantly fewer premature discontinuations for drug-related gastrointestinal or abnormal taste adverse events compared to BIAXIN tablets.

In community-acquired pneumonia studies conducted in adults comparing clarithromycin to erythromycin base or erythromycin stearate, there were fewer adverse events involving the digestive system in clarithromycin-treated patients compared to erythromycin-treated patients (13% vs 32%; p < 0.01). Twenty percent of erythromycin-treated patients discontinued therapy due to adverse events compared to 4% of clarithromycin-treated patients.

In two U.S. studies of acute otitis media comparing clarithromycin to amoxicillin/potassium clavulanate in pediatric patients, there were fewer adverse events involving the digestive system in clarithromycin-treated patients compared to amoxicillin/potassium clavulanate-treated patients (21% vs. 40%, p < 0.001). One-third as many clarithromycin-treated patients reported diarrhea as did amoxicillin/potassium clavulanate-treated patients.

Post-Marketing Experience

Allergic reactions ranging from urticaria and mild skin eruptions to rare cases of anaphylaxis, Stevens-Johnson syndrome, drug rash with eosinophilia and systemic symptoms (DRESS), Henoch-Schonlein Purpura and toxic epidermal necrolysis have occurred. Other spontaneously reported adverse events include glossitis, stomatitis, oral moniliasis, anorexia, vomiting, pancreatitis, tongue discoloration, thrombocytopenia, leukopenia, neutropenia, dizziness, myalgia and hemorrhage. There have been reports of tooth discoloration in patients treated with BIAXIN. Tooth discoloration is usually reversible with professional dental cleaning. There have been isolated reports of hearing loss, which is usually reversible, occurring chiefly in elderly women. Reports of alterations of the sense of smell including smell loss, usually in conjunction with taste perversion or taste loss, have also been reported.

Transient CNS events including anxiety, behavioral changes, confusional states, convulsions, depersonalization, disorientation, hallucinations, insomnia, depression, manic behavior, nightmares, psychosis, tinnitus, tremor, and vertigo have been reported during post-marketing surveillance. Events usually resolve with discontinuation of the drug.

Adverse reactions related to hepatic dysfunction have been reported in postmarketing experience with clarithromycin. (See WARNINGS – Hepatotoxicity).

There have been rare reports of hypoglycemia, some of which have occurred in patients taking oral hypoglycemic agents or insulin.

There have been post-marketing reports of BIAXIN XL tablets in the stool, many of which have occurred in patients with anatomic (including ileostomy or colostomy) or functional gastrointestinal disorders with shortened GI transit times.

As with other macrolides, clarithromycin has been associated with QT prolongation and ventricular arrhythmias, including ventricular tachycardia and torsades de pointes.

There have been reports of interstitial nephritis coincident with clarithromycin use.

There have been post-marketing reports of colchicine toxicity with concomitant use of clarithromycin and colchicine, especially in the elderly, some of which occurred in patients with renal insufficiency. Deaths have been reported in some such patients. (See WARNINGS and PRECAUTIONS.)

There have been reports of rhabdomyolysis coincident with clarithromycin use. In some reports, clarithromycin was administered concomitantly with statins, fibrates, colchicine or allopurinol.

Changes in laboratory values with possible clinical significance were as follows:

Hepatic

Elevated SGPT (ALT) < 1%; SGOT (AST) < 1%; GGT < 1%; alkaline phosphatase < 1%; LDH < 1%; total bilirubin < 1%

Hematologic

Decreased WBC < 1%; elevated prothrombin time 1%

Renal

Elevated BUN 4%; elevated serum creatinine < 1%

GGT, alkaline phosphatase, and prothrombin time data are from adult studies only.

OVERDOSAGE

Overdosage of clarithromycin can cause gastrointestinal symptoms such as abdominal pain, vomiting, nausea, and diarrhea.

Adverse reactions accompanying overdosage should be treated by the prompt elimination of unabsorbed drug and supportive measures. As with other macrolides, clarithromycin serum concentrations are not expected to be appreciably affected by hemodialysis or peritoneal dialysis.

DOSAGE AND ADMINISTRATION

BIAXIN Filmtab (clarithromycin tablets, USP) and BIAXIN Granules (clarithromycin for oral suspension, USP) may be given with or without food. BIAXIN XL Filmtab (clarithromycin extended-release tablets) should be taken with food. BIAXIN XL tablets should be swallowed whole and not chewed, broken or crushed.

Clarithromycin may be administered without dosage adjustment in the presence of hepatic impairment if there is normal renal function. In patients with severe renal impairment (CLCR < 30 mL/min), the dose of clarithromycin should be reduced by 50%. However, when patients with moderate or severe renal impairment are taking clarithromycin concomitantly with atazanavir or ritonavir, the dose of clarithromycin should be reduced by 50% or 75% for patients with CLCR of 30 to 60 mL/min or < 30 mL/min, respectively.

ADULT DOSAGE GUIDELINES
 | BIAXIN Tablets |  | BIAXIN XL Tablets
Infection | Dosage (q12h) | Duration (days) | Dosage (q24h) | Duration (days)
Pharyngitis/Tonsillitis due to
S. pyogenes | 250 mg | 10 | - | -
Acute maxillary sinusitis due to | 500 mg | 14 | 2 x 500 mg | 14
H. influenzae
M. catarrhalis
S. pneumoniae
Acute exacerbation of chronic bronchitis due to
H. influenzae | 500 mg | 7-14 | 2 x 500 mg | 7
H. parainfluenzae | 500 mg | 7 | 2 x 500 mg | 7
M. catarrhalis | 250 mg | 7-14 | 2 x 500 mg | 7
S. pneumoniae | 250 mg | 7-14 | 2 x 500 mg | 7
Community-Acquired Pneumonia due to
H. influenzae | 250 mg | 7 | 2 x 500 mg | 7
H. parainfluenzae | - | - | 2 x 500 mg | 7
M. catarrhalis | - | - | 2 x 500 mg | 7
S. pneumoniae | 250 mg | 7-14 | 2 x 500 mg | 7
C. pneumoniae | 250 mg | 7-14 | 2 x 500 mg | 7
M. pneumoniae | 250 mg | 7-14 | 2 x 500 mg | 7
Uncomplicated skin and skin structure | 250 mg | 7-14 | - | -
S. aureus
S. pyogenes

H. pylori Eradication to Reduce the Risk of Duodenal Ulcer Recurrence

Triple therapy: BIAXIN/lansoprazole/amoxicillin

The recommended adult dose is 500 mg BIAXIN, 30 mg lansoprazole, and 1 gram amoxicillin, all given twice daily (q12h) for 10 or 14 days. (See INDICATIONS AND USAGE and CLINICAL STUDIES sections.)

Triple therapy: BIAXIN/omeprazole/amoxicillin

The recommended adult dose is 500 mg BIAXIN, 20 mg omeprazole, and 1 gram amoxicillin, all given twice daily (q12h) for 10 days. (See INDICATIONS AND USAGE and CLINICAL STUDIES sections.) In patients with an ulcer present at the time of initiation of therapy, an additional 18 days of omeprazole 20 mg once daily is recommended for ulcer healing and symptom relief.

Dual therapy: BIAXIN/omeprazole

The recommended adult dose is 500 mg BIAXIN given three times daily (q8h) and 40 mg omeprazole given once daily (qAM) for 14 days. (See INDICATIONS AND USAGE and CLINICAL STUDIES sections.) An additional 14 days of omeprazole 20 mg once daily is recommended for ulcer healing and symptom relief.

Dual therapy: BIAXIN/ranitidine bismuth citrate

The recommended adult dose is 500 mg BIAXIN given twice daily (q12h) or three times daily (q8h) and 400 mg ranitidine bismuth citrate given twice daily (q12h) for 14 days. An additional 14 days of 400 mg twice daily is recommended for ulcer healing and symptom relief. BIAXIN and ranitidine bismuth citrate combination therapy is not recommended in patients with creatinine clearance less than 25 mL/min. (See INDICATIONS AND USAGE and CLINICAL STUDIES sections.)

Children

The usual recommended daily dosage is 15 mg/kg/day divided q12h for 10 days.

PEDIATRIC DOSAGE GUIDELINES
Based on Body Weight
Dosing Calculated on 7.5 mg/kg q12h
Weight |  | Dose
Kg | lbs | (q12h) | 125 mg/5 mL | 250 mg/5 mL
9 17 25 33 | 20 37 55 73 | 62.5 mg 125 mg 187.5 mg 250 mg | 2.5 mL q12h 5 mL q12h 7.5 mL q12h 10 mL q12h | 1.25 mL q12h 2.5 mL q12h 3.75 mL q12h 5 mL q12h

Mycobacterial Infections

Prophylaxis

The recommended dose of BIAXIN for the prevention of disseminated Mycobacterium avium disease is 500 mg b.i.d. In children, the recommended dose is 7.5 mg/kg b.i.d. up to 500 mg b.i.d. No studies of clarithromycin for MAC prophylaxis have been performed in pediatric populations and the doses recommended for prophylaxis are derived from MAC treatment studies in children. Dosing recommendations for children are in the table above.

Treatment

Clarithromycin is recommended as the primary agent for the treatment of disseminated infection due to Mycobacterium avium complex. Clarithromycin should be used in combination with other antimycobacterial drugs that have shown in vitro activity against MAC or clinical benefit in MAC treatment. (See CLINICAL STUDIES.) The recommended dose for mycobacterial infections in adults is 500 mg b.i.d. In children, the recommended dose is 7.5 mg/kg b.i.d. up to 500 mg b.i.d. Dosing recommendations for children are in the table above.

Clarithromycin therapy should continue for life if clinical and mycobacterial improvements are observed.

Constituting Instructions

The table below indicates the volume of water to be added when constituting:

Total Volume After Constitution | Clarithromycin Concentration After Constitution | Amount of Water to be Added*
50 mL | 125 mg/5 mL | 27 mL
100 mL | 125 mg/5 mL | 55 mL
50 mL | 250 mg/5 mL | 27 mL
100 mL | 250 mg/5 mL | 55 mL
* see instructions below.

Add half the volume of water to the bottle and shake vigorously. Add the remainder of water to the bottle and shake.

Shake well before each use. Oversize bottle provides shake space. Keep tightly closed. Do not refrigerate. After mixing, store at 15° to 30°C (59° to 86°F) and use within 14 days.

HOW SUPPLIED

BIAXIN XL Filmtab (clarithromycin extended-release tablets) are supplied as yellow oval film-coated 500 mg tablets debossed (on one side) with the Abbott logo and a two-letter Abbo-Code designation, KJ in the following packaging sizes:

500 mg tablets:

Bottles of 20 | NDC 54868-4191-0
Blister Pack of 14 | NDC 54868-4191-1

Store BIAXIN XL tablets at 20° to 25°C (68° to 77°F). Excursions permitted to 15° to 30°C (59° to 86°F). [See USP Controlled Room Temperature.]

BIAXIN Granules (clarithromycin for oral suspension, USP) is supplied in the following strengths and sizes:

Total Volume After Constitution | Clarithromycin Concentration After Constitution | Clarithromycin Contents Per Bottle | NDC
100 mL | 250 mg/5 mL | 5000 mg | 54868-3384-0

Store BIAXIN granules for oral suspension at controlled room temperature 15° to 30°C (59° to 86°F) in a well-closed container. Do not refrigerate BIAXIN suspension.

CLINICAL STUDIES

Mycobacterial Infections

Prophylaxis

A randomized, double-blind study (561) compared clarithromycin 500 mg b.i.d. to placebo in patients with CDC-defined AIDS and CD4 counts < 100 cells/µL. This study accrued 682 patients from November 1992 to January 1994, with a median CD4 cell count at study entry of 30 cells/µL. Median duration of clarithromycin was 10.6 months vs. 8.2 months for placebo. More patients in the placebo arm than the clarithromycin arm discontinued prematurely from the study (75.6% and 67.4%, respectively). However, if premature discontinuations due to MAC or death are excluded, approximately equal percentages of patients on each arm (54.8% on clarithromycin and 52.5% on placebo) discontinued study drug early for other reasons. The study was designed to evaluate the following endpoints:

1. MAC bacteremia, defined as at least one positive culture for M. avium complex bacteria from blood or another normally sterile site.
2. Survival.
3. Clinically significant disseminated MAC disease, defined as MAC bacteremia accompanied by signs or symptoms of serious MAC infection, including fever, night sweats, weight loss, anemia, or elevations in liver function tests.

MAC Bacteremia

In patients randomized to clarithromycin, the risk of MAC bacteremia was reduced by 69% compared to placebo. The difference between groups was statistically significant (p < 0.001). On an intent-to-treat basis, the one-year cumulative incidence of MAC bacteremia was 5.0% for patients randomized to clarithromycin and 19.4% for patients randomized to placebo. While only 19 of the 341 patients randomized to clarithromycin developed MAC, 11 of these cases were resistant to clarithromycin. The patients with resistant MAC bacteremia had a median baseline CD4 count of 10 cells/mm^3 (range 2 to 25 cells/mm^3). Information regarding the clinical course and response to treatment of the patients with resistant MAC bacteremia is limited. The 8 patients who received clarithromycin and developed susceptible MAC bacteremia had a median baseline CD4 count of 25 cells/mm^3 (range 10 to 80 cells/mm^3). Comparatively, 53 of the 341 placebo patients developed MAC; none of these isolates were resistant to clarithromycin. The median baseline CD4 count was 15 cells/mm^3 (range 2 to 130 cells/mm^3) for placebo patients that developed MAC.

Survival

A statistically significant survival benefit was observed.

Survival All Randomized Patients

 | Mortality |  | Reduction in
 | Placebo | Clarithromycin | Mortality on Clarithromycin
6 month | 9.4% | 6.5% | 31%
12 month | 29.7% | 20.5% | 31%
18 month | 46.4% | 37.5% | 20%

Since the analysis at 18 months includes patients no longer receiving prophylaxis the survival benefit of clarithromycin may be underestimated.

Clinically Significant Disseminated MAC Disease

In association with the decreased incidence of bacteremia, patients in the group randomized to clarithromycin showed reductions in the signs and symptoms of disseminated MAC disease, including fever, night sweats, weight loss, and anemia.

Safety

In AIDS patients treated with clarithromycin over long periods of time for prophylaxis against M. avium, it was often difficult to distinguish adverse events possibly associated with clarithromycin administration from underlying HIV disease or intercurrent illness. Median duration of treatment was 10.6 months for the clarithromycin group and 8.2 months for the placebo group.

Treatment-related* Adverse Event Incidence Rates (%) in Immunocompromised Adult Patients Receiving Prophylaxis Against M. avium Complex
Body System‡ Adverse Event | Clarithromycin (n = 339) % | Placebo (n = 339) %
Body as a Whole
Abdominal pain | 5.0% | 3.5%
Headache | 2.7% | 0.9%
Digestive
Diarrhea | 7.7% | 4.1%
Dyspepsia | 3.8% | 2.7%
Flatulence | 2.4% | 0.9%
Nausea | 11.2% | 7.1%
Vomiting | 5.9% | 3.2%
Skin & Appendages
Rash | 3.2% | 3.5%
Special Senses
Taste Perversion | 8.0% | 0.3%
* Includes those events possibly or probably related to study drug and excludes concurrent conditions.
‡ > 2% Adverse Event Incidence Rates for either treatment group.

Among these events, taste perversion was the only event that had significantly higher incidence in the clarithromycin-treated group compared to the placebo-treated group.

Discontinuation due to adverse events was required in 18% of patients receiving clarithromycin compared to 17% of patients receiving placebo in this trial. Primary reasons for discontinuation in clarithromycin treated patients include headache, nausea, vomiting, depression and taste perversion.

Changes in Laboratory Values of Potential Clinical Importance

In immunocompromised patients receiving prophylaxis against M. avium, evaluations of laboratory values were made by analyzing those values outside the seriously abnormal value (i.e., the extreme high or low limit) for the specified test.

Percentage of Patients(a) Exceeding Extreme Laboratory Value in Patients Receiving Prophylaxis Against M. avium Complex
 |  | Clarithromycin 500 mg b.i.d. | Placebo
Hemoglobin | < 8 g/dL | 4/118 3% | 5/103 5%
Platelet Count | < 50 x 10^9/L | 11/249 4% | 12/250 5%
WBC Count | < 1 x 10^9/L | 2/103 4% | 0/95 0%
SGOT | > 5 x ULN(b) | 7/196 4% | 5/208 2%
SGPT | > 5 x ULN(b) | 6/217 3% | 4/232 2%
Alk. Phos. | > 5 x ULN(b) | 5/220 2% | 5/218 2%
(a) Includes only patients with baseline values within the normal range or borderline high (hematology variables) and within the normal range or borderline low (chemistry variables).
(b) ULN = Upper Limit of Normal

Treatment

Three randomized studies (500, 577, and 521) compared different dosages of clarithromycin in patients with CDC-defined AIDS and CD4 counts < 100 cells/µL. These studies accrued patients from May 1991 to March 1992. Study 500 was randomized, double-blind; Study 577 was open-label compassionate use. Both studies used 500 and 1000 mg b.i.d. doses; Study 500 also had a 2000 mg b.i.d. group. Study 521 was a pediatric study at 3.75, 7.5, and 15 mg/kg b.i.d. Study 500 enrolled 154 adult patients, Study 577 enrolled 469 adult patients, and Study 521 enrolled 25 patients between the ages of 1 to 20. The majority of patients had CD4 cell counts < 50/µL at study entry. The studies were designed to evaluate the following end points:

1. Change in MAC bacteremia or blood cultures negative for M. avium.

2. Change in clinical signs and symptoms of MAC infection including one or more of the following: fever, night sweats, weight loss, diarrhea, splenomegaly, and hepatomegaly.

The results for the 500 study are described below. The 577 study results were similar to the results of the 500 study. Results with the 7.5 mg/kg b.i.d. dose in the pediatric study were comparable to those for the 500 mg b.i.d. regimen in the adult studies.

Study 069 compared the safety and efficacy of clarithromycin in combination with ethambutol versus clarithromycin in combination with ethambutol and clofazimine for the treatment of disseminated MAC (dMAC) infection.^4 This 24-week study enrolled 106 patients with AIDS and dMAC, with 55 patients randomized to receive clarithromycin and ethambutol, and 51 patients randomized to receive clarithromycin, ethambutol, and clofazimine. Baseline characteristics between study arms were similar with the exception of median CFU counts being at least 1 log higher in the clarithromycin, ethambutol, and clofazimine arm.

Compared to prior experience with clarithromycin monotherapy, the two-drug regimen of clarithromycin and ethambutol was well tolerated and extended the time to microbiologic relapse, largely through suppressing the emergence of clarithromycin resistant strains. However, the addition of clofazimine to the regimen added no additional microbiologic or clinical benefit. Tolerability of both multidrug regimens was comparable with the most common adverse events being gastrointestinal in nature. Patients receiving the clofazimine-containing regimen had reduced survival rates; however, their baseline mycobacterial colony counts were higher. The results of this trial support the addition of ethambutol to clarithromycin for the treatment of initial dMAC infections but do not support adding clofazimine as a third agent.

MAC Bacteremia

Decreases in MAC bacteremia or negative blood cultures were seen in the majority of patients in all dose groups. Mean reductions in colony forming units (CFU) are shown below. Included in the table are results from a separate study with a four drug regimen^5 (ciprofloxacin, ethambutol, rifampicin, and clofazimine). Since patient populations and study procedures may vary between these two studies, comparisons between the clarithromycin results and the combination therapy results should be interpreted cautiously.

Mean Reductions in Log CFU from Baseline (After 4 Weeks of Therapy)
500 mg b.i.d. (N = 35) | 1000 mg b.i.d. (N = 32) | 2000 mg b.i.d. (N = 26) | Four Drug Regimen (N = 24)
1.5 | 2.3 | 2.3 | 1.4

Although the 1000 mg and 2000 mg b.i.d. doses showed significantly better control of bacteremia during the first four weeks of therapy, no significant differences were seen beyond that point. The percent of patients whose blood was sterilized as shown by one or more negative cultures at any time during acute therapy was 61% (30/49) for the 500 mg b.i.d. group and 59% (29/49) and 52% (25/48) for the 1000 and 2000 mg b.i.d. groups, respectively. The percent of patients who had 2 or more negative cultures during acute therapy that were sustained through study Day 84 was 25% (12/49) in both the 500 and 1000 mg b.i.d. groups and 8% (4/48) for the 2000 mg b.i.d. group. By Day 84, 23% (11/49), 37% (18/49), and 56% (27/48) of patients had died or discontinued from the study, and 14% (7/49), 12% (6/49), and 13% (6/48) of patients had relapsed in the 500, 1000, and 2000 mg b.i.d. dose groups, respectively. All of the isolates had an MIC < 8 µg/mL at pre-treatment. Relapse was almost always accompanied by an increase in MIC. The median time to first negative culture was 54, 41, and 29 days for the 500, 1000, and 2000 mg b.i.d. groups, respectively. The time to first decrease of at least 1 log in CFU count was significantly shorter with the 1000 and 2000 mg b.i.d. doses (median equal to 16 and 15 days, respectively) in comparison to the 500 mg b.i.d. group (median equal to 29 days). The median time to first positive culture or study discontinuation following the first negative culture was 43, 59 and 43 days for the 500, 1000, and 2000 mg b.i.d. groups, respectively.

Clinically Significant Disseminated MAC Disease

Among patients experiencing night sweats prior to therapy, 84% showed resolution or improvement at some point during the 12 weeks of clarithromycin at 500 to 2000 mg b.i.d. doses. Similarly, 77% of patients reported resolution or improvement in fevers at some point. Response rates for clinical signs of MAC are given below:

Resolution of Fever |  |  | Resolution of Night Sweats
b.i.d. dose (mg) | % ever afebrile | % afebrile ≥ 6 weeks | b.i.d. dose (mg) | % ever resolving | % resolving ≥ 6 weeks
500 | 67% | 23% | 500 | 85% | 42%
1000 | 67% | 12% | 1000 | 70% | 33%
2000 | 62% | 22% | 2000 | 72% | 36%

Weight Gain > 3% |  |  | Hemoglobin Increase > 1 gm
b.i.d. dose (mg) | % ever gaining | % gaining ≥ 6 weeks | b.i.d. dose (mg) | % ever increasing | % increasing ≥ 6 weeks
500 | 33% | 14% | 500 | 58% | 26%
1000 | 26% | 17% | 1000 | 37% | 6%
2000 | 26% | 12% | 2000 | 62% | 18%

The median duration of response, defined as improvement or resolution of clinical signs and symptoms, was 2 to 6 weeks.

Since the study was not designed to determine the benefit of monotherapy beyond 12 weeks, the duration of response may be underestimated for the 25 to 33% of patients who continued to show clinical response after 12 weeks.

Survival

Median survival time from study entry (Study 500) was 249 days at the 500 mg b.i.d. dose compared to 215 days with the 1000 mg b.i.d. dose. However, during the first 12 weeks of therapy, there were 2 deaths in 53 patients in the 500 mg b.i.d. group versus 13 deaths in 51 patients in the 1000 mg b.i.d. group. The reason for this apparent mortality difference is not known. Survival in the two groups was similar beyond 12 weeks. The median survival times for these dosages were similar to recent historical controls with MAC when treated with combination therapies.^5

Median survival time from study entry in Study 577 was 199 days for the 500 mg b.i.d. dose and 179 days for the 1000 mg b.i.d. dose. During the first four weeks of therapy, while patients were maintained on their originally assigned dose, there were 11 deaths in 255 patients taking 500 mg b.i.d. and 18 deaths in 214 patients taking 1000 mg b.i.d.

Safety

The adverse event profiles showed that both the 500 and 1000 mg b.i.d. doses were well tolerated. The 2000 mg b.i.d. dose was poorly tolerated and resulted in a higher proportion of premature discontinuations.

In AIDS patients and other immunocompromised patients treated with the higher doses of clarithromycin over long periods of time for mycobacterial infections, it was often difficult to distinguish adverse events possibly associated with clarithromycin administration from underlying signs of HIV disease or intercurrent illness.

The following analyses summarize experience during the first 12 weeks of therapy with clarithromycin. Data are reported separately for Study 500 (randomized, double-blind) and Study 577 (open-label, compassionate use) and also combined. Adverse events were reported less frequently in Study 577, which may be due in part to differences in monitoring between the two studies. In adult patients receiving clarithromycin 500 mg b.i.d., the most frequently reported adverse events, considered possibly or probably related to study drug, with an incidence of 5% or greater, are listed below. Most of these events were mild to moderate in severity, although 5% (Study 500: 8%; Study 577: 4%) of patients receiving 500 mg b.i.d. and 5% (Study 500: 4%; Study 577: 6%) of patients receiving 1000 mg b.i.d. reported severe adverse events. Excluding those patients who discontinued therapy or died due to complications of their underlying non-mycobacterial disease, approximately 8% (Study 500: 15%; Study 577: 7%) of the patients who received 500 mg b.i.d. and 12% (Study 500: 14%; Study 577: 12%) of the patients who received 1000 mg b.i.d. discontinued therapy due to drug-related events during the first 12 weeks of therapy. Overall, the 500 and 1000 mg b.i.d. doses had similar adverse event profiles.

Treatment-related* Adverse Event Incidence Rates (%) in Immunocompromised Adult Patients During the First 12 Weeks of Therapy with 500 mg b.i.d. Clarithromycin Dose
Adverse Event | Study 500 (n = 53) | Study 577 (n = 255) | Combined (n = 308)
Abdominal Pain | 7.5 | 2.4 | 3.2
Diarrhea | 9.4 | 1.6 | 2.9
Flatulence | 7.5 | 0.0 | 1.3
Headache | 7.5 | 0.4 | 1.6
Nausea | 28.3 | 9.0 | 12.3
Rash | 9.4 | 2.0 | 3.2
Taste Perversion | 18.9 | 0.4 | 3.6
Vomiting | 24.5 | 3.9 | 7.5
* Includes those events possibly or probably related to study drug and excludes concurrent conditions.

A limited number of pediatric AIDS patients have been treated with clarithromycin suspension for mycobacterial infections. The most frequently reported adverse events, excluding those due to the patient's concurrent condition, were consistent with those observed in adult patients.

Changes in Laboratory Values

In immunocompromised patients treated with clarithromycin for mycobacterial infections, evaluations of laboratory values were made by analyzing those values outside the seriously abnormal level (i.e., the extreme high or low limit) for the specified test.

Percentage of Patients(a) Exceeding Extreme Laboratory Value Limits During First 12 Weeks of Treatment 500 mg b.i.d. Dose(b)
 |  | Study 500 | Study 577 | Combined
BUN | > 50 mg/dL | 0% | < 1% | < 1%
Platelet Count | < 50 x 10^9/L | 0% | < 1% | < 1%
SGOT | > 5 x ULN(c) | 0% | 3% | 2%
SGPT | > 5 x ULN(c) | 0% | 2% | 1%
WBC | < 1 x 10^9/L | 0% | 1% | 1%
(a) Includes only patients with baseline values within the normal range or borderline high (hematology variables) and within the normal range or borderline low (chemistry variables)
(b) Includes all values within the first 12 weeks for patients who start on 500 mg b.i.d.
(c) ULN = Upper Limit of Normal

Otitis Media

In a controlled clinical study of acute otitis media performed in the United States, where significant rates of beta-lactamase producing organisms were found, clarithromycin was compared to an oral cephalosporin. In this study, very strict evaluability criteria were used to determine clinical response. For the 223 patients who were evaluated for clinical efficacy, the clinical success rate (i.e., cure plus improvement) at the post-therapy visit was 88% for clarithromycin and 91% for the cephalosporin.

In a smaller number of patients, microbiologic determinations were made at the pre-treatment visit. The following presumptive bacterial eradication/clinical cure outcomes (i.e., clinical success) were obtained:

U.S. Acute Otitis Media Study Clarithromycin vs. Oral Cephalosporin EFFICACY RESULTS
PATHOGEN | OUTCOME
S. pneumoniae | clarithromycin success rate, 13/15 (87%), control 4/5
H. influenzae* | clarithromycin success rate, 10/14 (71%), control 3/4
M. catarrhalis | clarithromycin success rate, 4/5,control 1/1
S. pyogenes | clarithromycin success rate, 3/3,control 0/1
Overall | clarithromycin success rate, 30/37 (81%), control 8/11 (73%)
* None of the H. influenzae isolated pre-treatment was resistant to clarithromycin; 6% were resistant to the control agent.

Safety

The incidence of adverse events in all patients treated, primarily diarrhea and vomiting, did not differ clinically or statistically for the two agents.

In two other controlled clinical trials of acute otitis media performed in the United States, where significant rates of beta-lactamase producing organisms were found, clarithromycin was compared to an oral antimicrobial agent that contained a specific beta-lactamase inhibitor. In these studies, very strict evaluability criteria were used to determine the clinical responses. In the 233 patients who were evaluated for clinical efficacy, the combined clinical success rate (i.e., cure and improvement) at the post-therapy visit was 91% for both clarithromycin and the control.

For the patients who had microbiologic determinations at the pre-treatment visit, the following presumptive bacterial eradication/clinical cure outcomes (i.e., clinical success) were obtained:

Two U.S. Acute Otitis Media Studies Clarithromycin vs. Antimicrobial/Beta-lactamase Inhibitor EFFICACY RESULTS
PATHOGEN | OUTCOME
S. pneumoniae | clarithromycin success rate, 43/51 (84%), control 55/56 (98%)
H. influenzae* | clarithromycin success rate, 36/45 (80%), control 31/33 (94%)
M. catarrhalis | clarithromycin success rate, 9/10 (90%), control 6/6
S. pyogenes | clarithromycin success rate, 3/3, control 5/5
Overall | clarithromycin success rate, 91/109 (83%), control 97/100 (97%)
* Of the H. influenzae isolated pre-treatment, 3% were resistant to clarithromycin and 10% were resistant to the control agent.

Safety

The incidence of adverse events in all patients treated, primarily diarrhea (15% vs. 38%) and diaper rash (3% vs. 11%) in young children, was clinically and statistically lower in the clarithromycin arm versus the control arm.

Duodenal Ulcer Associated with H. pylori Infection

Clarithromycin + Lansoprazole and Amoxicillin

H. pylori Eradication for Reducing the Risk of Duodenal Ulcer Recurrence

Two U.S. randomized, double-blind clinical studies in patients with H. pylori and duodenal ulcer disease (defined as an active ulcer or history of an active ulcer within one year) evaluated the efficacy of clarithromycin in combination with lansoprazole and amoxicillin capsules as triple 14-day therapy for eradication of H. pylori. Based on the results of these studies, the safety and efficacy of the following eradication regimen were established:

Triple therapy: BIAXIN (clarithromycin) 500 mg b.i.d. + lansoprazole 30 mg b.i.d. + amoxicillin 1 gm b.i.d.

Treatment was for 14 days. H. pylori eradication was defined as two negative tests (culture and histology) at 4 to 6 weeks following the end of treatment.

The combination of BIAXIN plus lansoprazole and amoxicillin as triple therapy was effective in eradicating H. pylori. Eradication of H. pylori has been shown to reduce the risk of duodenal ulcer recurrence.

A randomized, double-blind clinical study performed in the U.S. in patients with H. pylori and duodenal ulcer disease (defined as an active ulcer or history of an ulcer within one year) compared the efficacy of clarithromycin in combination with lansoprazole and amoxicillin as triple therapy for 10 and 14 days. This study established that the 10-day triple therapy was equivalent to the 14-day triple therapy in eradicating H. pylori.

H. pylori Eradication Rates-Triple Therapy (BIAXIN/lansoprazole/amoxicillin) Percent of Patients Cured [95% Confidence Interval] (number of patients)
Study | Duration | Triple Therapy Evaluable Analysis* | Triple Therapy Intent-to-Treat Analysis#
M93-131 | 14 days | 92† [80.0-97.7] (n = 48) | 86† [73.3-93.5] (n = 55)
M95-392 | 14 days | 86‡ [75.7-93.6] (n = 66) | 83‡ [72.0-90.8] (n = 70)
M95-399¶ | 14 days | 85 [77.0-91.0] (N = 113) | 82 [73.9-88.1] (N = 126)
 | 10 days | 84 [76.0-89.8] (N = 123) | 81 [73.9-87.6] (N = 135)
* Based on evaluable patients with confirmed duodenal ulcer (active or within one year) and H. pylori infection at baseline defined as at least two of three positive endoscopic tests from CLOtest (Delta West LTD., Bentley, Australia), histology, and/or culture. Patients were included in the analysis if they completed the study. Additionally, if patients were dropped out of the study due to an adverse event related to the study drug, they were included in the analysis as evaluable failures of therapy.
# Patients were included in the analysis if they had documented H. pylori infection at baseline as defined above and had a confirmed duodenal ulcer (active or within one year). All dropouts were included as failures of therapy.
† (p < 0.05) versus BIAXIN/lansoprazole and lansoprazole/amoxicillin dual therapy.
‡ (p < 0.05) versus BIAXIN/amoxicillin dual therapy.
¶ The 95% confidence interval for the difference in eradication rates, 10-day minus 14-day, is (-10.5, 8.1) in the evaluable analysis and (-9.7, 9.1) in the intent-to-treat analysis.

Clarithromycin + Omeprazole and Amoxicillin Therapy

H. pylori Eradication for Reducing the Risk of Duodenal Ulcer Recurrence

Three U.S., randomized, double-blind clinical studies in patients with H. pylori infection and duodenal ulcer disease (n = 558) compared clarithromycin plus omeprazole and amoxicillin to clarithromycin plus amoxicillin. Two studies (Studies 126 and 127) were conducted in patients with an active duodenal ulcer, and the third study (Study 446) was conducted in patients with a duodenal ulcer in the past 5 years, but without an ulcer present at the time of enrollment. The dosage regimen in the studies was clarithromycin 500 mg b.i.d. plus omeprazole 20 mg b.i.d. plus amoxicillin 1 gram b.i.d. for 10 days. In Studies 126 and 127, patients who took the omeprazole regimen also received an additional 18 days of omeprazole 20 mg q.d. Endpoints studied were eradication of H. pylori and duodenal ulcer healing (studies 126 and 127 only). H. pylori status was determined by CLOtest®, histology, and culture in all three studies. For a given patient, H. pylori was considered eradicated if at least two of these tests were negative, and none was positive. The combination of clarithromycin plus omeprazole and amoxicillin was effective in eradicating H. pylori.

Per-Protocol and Intent-to-Treat H. pylori Eradication Rates % of Patients Cured [95% Confidence Interval]
 | Clarithromycin + omeprazole + amoxicillin |  | Clarithromycin + amoxicillin
 | Per-Protocol † | Intent-to-Treat ‡ | Per-Protocol † | Intent-to-Treat ‡
Study 126 | *77 [64, 86] (n = 64) | 69 [57, 79] (n = 80) | 43 [31, 56] (n = 67) | 37 [27, 48] (n = 84)
Study 127 | *78 [67, 88] (n = 65) | 73 [61, 82] (n = 77) | 41 [29, 54] (n = 68) | 36 [26, 47] (n = 84)
Study M96-446 | *90 [80, 96] (n = 69) | 83 [74, 91] (n = 84) | 33 [24, 44] (n = 93) | 32 [23, 42] (n = 99)
† Patients were included in the analysis if they had confirmed duodenal ulcer disease (active ulcer studies 126 and 127; history of ulcer within 5 years, study M96-446) and H. pylori infection at baseline defined as at least two of three positive endoscopic tests from CLOtest®, histology, and/or culture. Patients were included in the analysis if they completed the study. Additionally, if patients dropped out of the study due to an adverse event related to the study drug, they were included in the analysis as failures of therapy. The impact of eradication on ulcer recurrence has not been assessed in patients with a past history of ulcer.
‡ Patients were included in the analysis if they had documented H. pylori infection at baseline and had confirmed duodenal ulcer disease. All dropouts were included as failures of therapy.
* p < 0.05 versus clarithromycin plus amoxicillin.

Safety

In clinical trials using combination therapy with clarithromycin plus omeprazole and amoxicillin, no adverse reactions peculiar to the combination of these drugs have been observed. Adverse reactions that have occurred have been limited to those that have been previously reported with clarithromycin, omeprazole, or amoxicillin.

The most frequent adverse experiences observed in clinical trials using combination therapy with clarithromycin plus omeprazole and amoxicillin (n = 274) were diarrhea (14%), taste perversion (10%), and headache (7%).

For information about adverse reactions with omeprazole or amoxicillin, refer to the ADVERSE REACTIONS section of their package inserts.

Clarithromycin + Omeprazole Therapy

Four randomized, double-blind, multi-center studies (067, 100, 812b, and 058) evaluated clarithromycin 500 mg t.i.d. plus omeprazole 40 mg q.d. for 14 days, followed by omeprazole 20 mg q.d. (067, 100, and 058) or by omeprazole 40 mg q.d. (812b) for an additional 14 days in patients with active duodenal ulcer associated with H. pylori . Studies 067 and 100 were conducted in the U.S. and Canada and enrolled 242 and 256 patients, respectively. H. pylori infection and duodenal ulcer were confirmed in 219 patients in Study 067 and 228 patients in Study 100. These studies compared the combination regimen to omeprazole and clarithromycin monotherapies. Studies 812b and 058 were conducted in Europe and enrolled 154 and 215 patients, respectively. H. pylori infection and duodenal ulcer were confirmed in 148 patients in Study 812b and 208 patients in Study 058. These studies compared the combination regimen to omeprazole monotherapy. The results for the efficacy analyses for these studies are described below.

Duodenal Ulcer Healing

The combination of clarithromycin and omeprazole was as effective as omeprazole alone for healing duodenal ulcer.

End-of-Treatment Ulcer Healing Rates Percent of Patients Healed (n/N)
Study | Clarithromycin + Omeprazole | Omeprazole | Clarithromycin
U.S. Studies
Study 100 | 94% (58/62)† | 88% (60/68) | 71% (49/69)
Study 067 | 88% (56/64)† | 85% (55/65) | 64% (44/69)
Non-U.S. Studies
Study 058 | 99% (84/85) | 95% (82/86) | N/A
Study 812b^1 | 100% (64/64) | 99% (71/72) | N/A
† p < 0.05 for clarithromycin + omeprazole versus clarithromycin monotherapy.
1 In Study 812b patients received omeprazole 40 mg daily for days 15 to 28.

Eradication of H. pylori Associated with Duodenal Ulcer

The combination of clarithromycin and omeprazole was effective in eradicating H. pylori.

H. pylori Eradication Rates (Per-Protocol Analysis) at 4 to 6 weeks Percent of Patients Cured (n/N)
Study | Clarithromycin + Omeprazole | Omeprazole | Clarithromycin
U.S. Studies
Study 100 | 64% (39/61)†‡ | 0% (0/59) | 39% (17/44)
Study 067 | 74% (39/53)†‡ | 0% (0/54) | 31% (13/42)
Non-U.S. Studies
Study 058 | 74% (64/86)‡ | 1% (1/90) | N/A
Study 812b | 83% (50/60)‡ | 1% (1/74) | N/A
† Statistically significantly higher than clarithromycin monotherapy (p < 0.05).
‡ Statistically significantly higher than omeprazole monotherapy (p < 0.05).

H. pylori eradication was defined as no positive test (culture or histology) at 4 weeks following the end of treatment, and two negative tests were required to be considered eradicated. In the per-protocol analysis, the following patients were excluded: dropouts, patients with major protocol violations, patients with missing H. pylori tests post-treatment, and patients that were not assessed for H. pylori eradication at 4 weeks after the end of treatment because they were found to have an unhealed ulcer at the end of treatment.

Ulcer recurrence at 6-months following the end of treatment was assessed for patients in whom ulcers were healed post-treatment.

Ulcer Recurrence at 6 months by H. pylori Status at 4-6 Weeks
 |  | H. pylori Negative | H. pylori Positive
U.S. Studies
Study 100
Clarithromycin + Omeprazole |  | 6% (2/34) | 56% (9/16)
Omeprazole |  | - (0/0) | 71% (35/49)
Clarithromycin |  | 12% (2/17) | 32% (7/22)
Study 067
Clarithromycin + Omeprazole |  | 38% (11/29) | 50% (6/12)
Omeprazole |  | - (0/0) | 67% (31/46)
Clarithromycin |  | 18% (2/11) | 52% (14/27)
Non-U.S. Studies
Study 058
Clarithromycin + Omeprazole |  | 6% (3/53) | 24% (4/17)
Omeprazole |  | 0% (0/3) | 55% (39/71)
Study 812b*
Clarithromycin + Omeprazole |  | 5% (2/42) | 0% (0/7)
Omeprazole |  | 0% (0/1) | 54% (32/59)
*12-month recurrence rates:
Clarithromycin + Omeprazole |  | 3% (1/40) | 0% (0/6)
Omeprazole |  | 0% (0/1) | 67% (29/43)

Thus, in patients with duodenal ulcer associated with H. pylori infection, eradication of H. pylori reduced ulcer recurrence.

Safety

The adverse event profiles for the four studies showed that the combination of clarithromycin 500 mg t.i.d. and omeprazole 40 mg q.d. for 14 days, followed by omeprazole 20 mg q.d. (067, 100, and 058) or 40 mg q.d. (812b) for an additional 14 days was well tolerated. Of the 346 patients who received the combination, 12 (3.5%) patients discontinued study drug due to adverse events.

Adverse Events with an Incidence of 3% or Greater
Adverse Event | Clarithromycin + Omeprazole (N = 346) % of Patients | Omeprazole (N = 355) % of Patients | Clarithromycin (N = 166) % of Patients*
Taste Perversion | 15% | 1% | 16%
Nausea | 5% | 1% | 3%
Headache | 5% | 6% | 9%
Diarrhea | 4% | 3% | 7%
Vomiting | 4% | < 1% | 1%
Abdominal Pain | 3% | 2% | 1%
Infection | 3% | 4% | 2%
* Studies 067 and 100, only.

Most of these events were mild to moderate in severity.

Changes in laboratory values with possible clinical significance in patients taking clarithromycin and omeprazole were as follows:

Hepatic - elevated direct bilirubin < 1%; GGT < 1%; SGOT (AST) < 1%; SGPT (ALT) < 1%.

Renal - elevated serum creatinine < 1%.

For information on omeprazole, refer to the ADVERSE REACTIONS section of the PRILOSEC package insert.

Clarithromycin + Ranitidine Bismuth Citrate Therapy

In a U.S. double-blind, randomized, multicenter, dose-comparison trial, ranitidine bismuth citrate 400 mg b.i.d. for 4 weeks plus clarithromycin 500 mg b.i.d. for the first 2 weeks was found to have an equivalent H. pylori eradication rate (based on culture and histology) when compared to ranitidine bismuth citrate 400 mg b.i.d. for 4 weeks plus clarithromycin 500 mg t.i.d. for the first 2 weeks. The intent-to-treat H. pylori eradication rates are shown below:

H. pylori Eradication Rates in Study H2BA-3001
Analysis | RBC 400 mg + Clarithromycin 500 mg b.i.d. | RBC 400 mg + Clarithromycin 500 mg t.i.d. | 95% CI Rate Difference
ITT | 65% (122/188) [58%, 72%] | 63% (122/195) [55%, 69%] | (-8%, 12%)
Per-Protocol | 72% (117/162) [65%, 79%] | 71% (120/170) [63%, 77%] | (-9%, 12%)

H. pylori eradication was defined as no positive test at 4 weeks following the end of treatment. Patients must have had two tests performed, and these must have been negative to be considered eradicated of H. pylori. The following patients were excluded from the per-protocol analysis: patients not infected with H. pylori prestudy, dropouts, patients with major protocol violations, patients with missing H. pylori tests. Patients excluded from the intent-to-treat analysis included those not infected with H. pylori prestudy and those with missing H. pylori tests prestudy. Patients were assessed for H. pylori eradication (4 weeks following treatment) regardless of their healing status (at the end of treatment).

The relationship between H. pylori eradication and duodenal ulcer recurrence was assessed in a combined analysis of six U.S. randomized, double-blind, multicenter, placebo-controlled trials using ranitidine bismuth citrate with or without antibiotics. The results from approximately 650 U.S. patients showed that the risk of ulcer recurrence within 6 months of completing treatment was two times less likely in patients whose H. pylori infection was eradicated compared to patients in whom H. pylori infection was not eradicated.

Safety

In clinical trials using combination therapy with clarithromycin plus ranitidine bismuth citrate, no adverse reactions peculiar to the combination of these drugs (using clarithromycin twice daily or three times a day) were observed. Adverse reactions that have occurred have been limited to those reported with clarithromycin or ranitidine bismuth citrate. (See ADVERSE REACTIONS section of the Tritec package insert.) The most frequent adverse experiences observed in clinical trials using combination therapy with clarithromycin (500 mg three times a day) with ranitidine bismuth citrate (n = 329) were taste disturbance (11%), diarrhea (5%), nausea and vomiting (3%). The most frequent adverse experiences observed in clinical trials using combination therapy with clarithromycin (500 mg twice daily) with ranitidine bismuth citrate (n = 196) were taste disturbance (8%), nausea and vomiting (5%), and diarrhea (4%).

ANIMAL PHARMACOLOGY AND TOXICOLOGY

Clarithromycin is rapidly and well-absorbed with dose-linear kinetics, low protein binding, and a high volume of distribution. Plasma half-life ranged from 1 to 6 hours and was species dependent. High tissue concentrations were achieved, but negligible accumulation was observed. Fecal clearance predominated. Hepatotoxicity occurred in all species tested (i.e., in rats and monkeys at doses 2 times greater than and in dogs at doses comparable to the maximum human daily dose, based on mg/m^2). Renal tubular degeneration (calculated on a mg/m^2 basis) occurred in rats at doses 2 times, in monkeys at doses 8 times, and in dogs at doses 12 times greater than the maximum human daily dose. Testicular atrophy (on a mg/m^2 basis) occurred in rats at doses 7 times, in dogs at doses 3 times, and in monkeys at doses 8 times greater than the maximum human daily dose. Corneal opacity (on a mg/m^2 basis) occurred in dogs at doses 12 times and in monkeys at doses 8 times greater than the maximum human daily dose. Lymphoid depletion (on a mg/m^2 basis) occurred in dogs at doses 3 times greater than and in monkeys at doses 2 times greater than the maximum human daily dose. These adverse events were absent during clinical trials.

REFERENCES

1. National Committee for Clinical Laboratory Standards, Methods for Dilution Antimicrobial Susceptibility Tests for Bacteria that Grow Aerobically - Fourth Edition. Approved Standard NCCLS Document M7-A4, Vol. 17, No. 2, NCCLS, Wayne, PA, January, 1997.
2. National Committee for Clinical Laboratory Standards, Performance Standards for Antimicrobial Disk Susceptibility Tests - Sixth Edition. Approved Standard NCCLS Document M2-A6, Vol. 17, No. 1, NCCLS, Wayne, PA, January, 1997.
3. National Committee for Clinical Laboratory Standards. Summary Minutes, Subcommittee on Antimicrobial Susceptibility Testing, Tampa, FL. January 11-13, 1998.
4. Chaisson RE, et al. Clarithromycin and Ethambutol with or without Clofazimine for the Treatment of Bacteremic Mycobacterium avium Complex Disease in Patients with HIV Infection. AIDS. 1997;11:311-317.
5. Kemper CA, et al. Treatment of Mycobacterium avium Complex Bacteremia in AIDS with a Four-Drug Oral Regimen. Ann Intern Med. 1992;116:466-472.

Filmtab – Film-sealed tablets, Abbott

Biaxin Filmtab 250 mg and 500 mg and Biaxin XL 500 mg
Mfd. by Abbott Pharmaceuticals PR Ltd., Barceloneta, PR 00617

Biaxin Granules for Oral Suspension, 125mg/5mL and 250mg/5mL
Mfd. by Abbott Laboratories, North Chicago, IL 60064

For Abbott Laboratories, North Chicago, IL 60064, U.S.A.

Revised: 11/2011 Abbott Laboratories

Relabeling and Repackaging by:
Physicians Total Care, Inc.
Tulsa, Oklahoma 74146

PACKAGE LABEL

NDC 54868-4191-0

20 Tablets

BIAXIN® XL

FILMTAB®

clarithromycin extended-release tablets

500 mg

Rx only

NDC 54868-3384-0

100 mL (when mixed)

BIAXIN® GRANULES

clarithromycin for oral suspension, USP

250 mg per 5 mL when reconstituted

Rx only